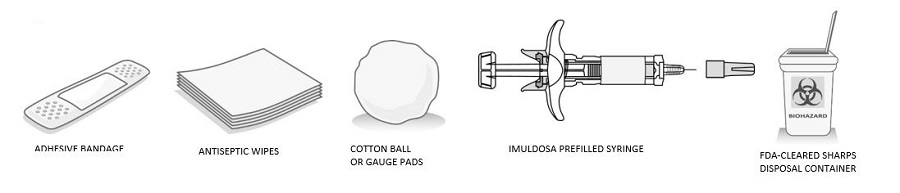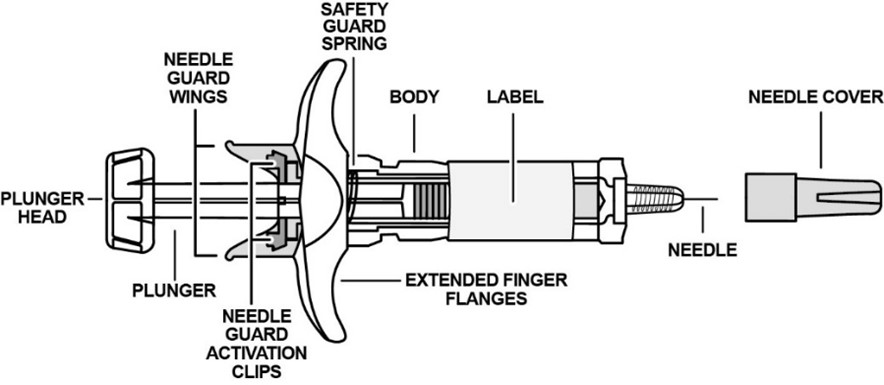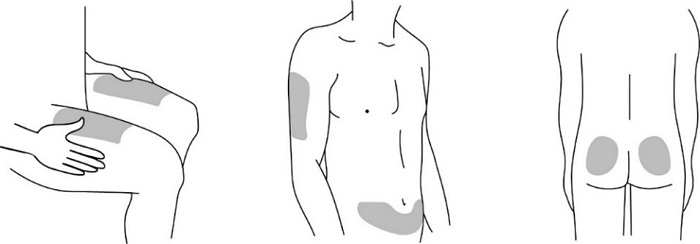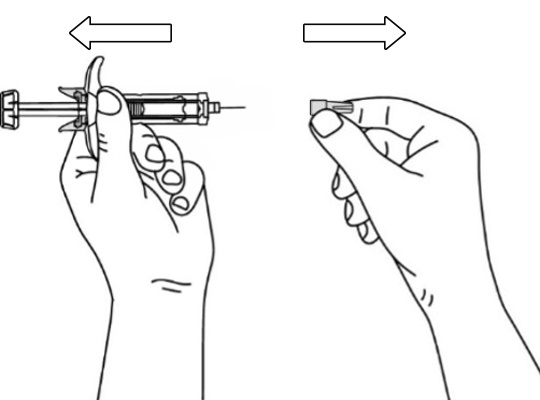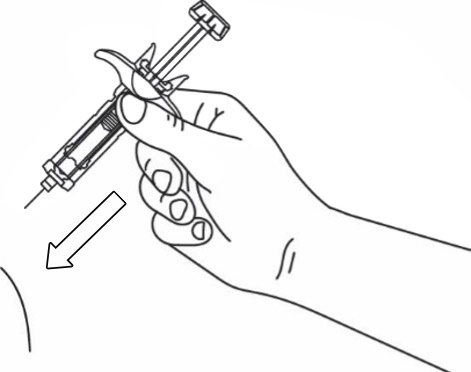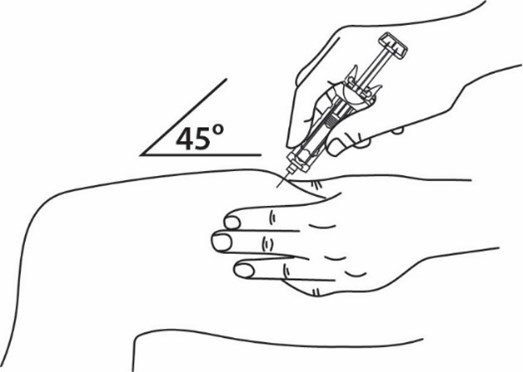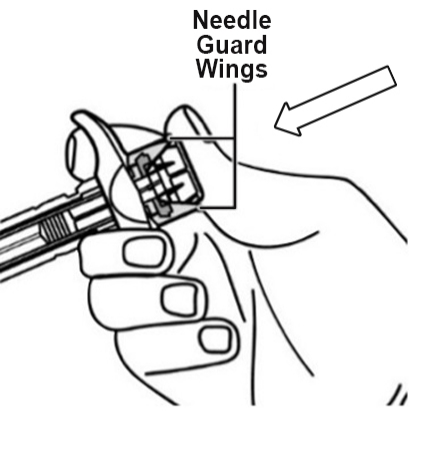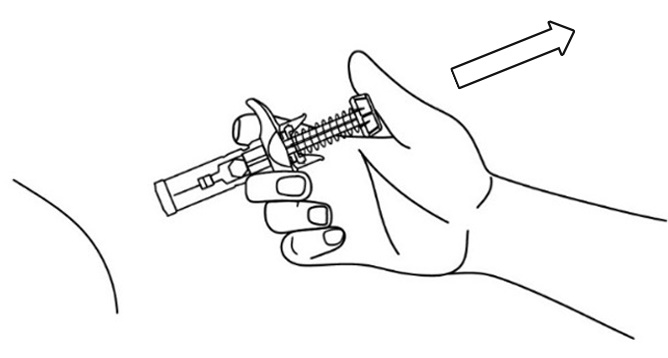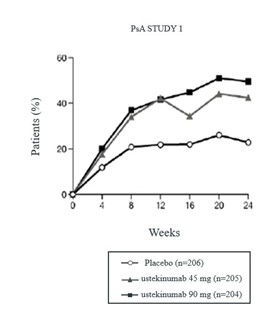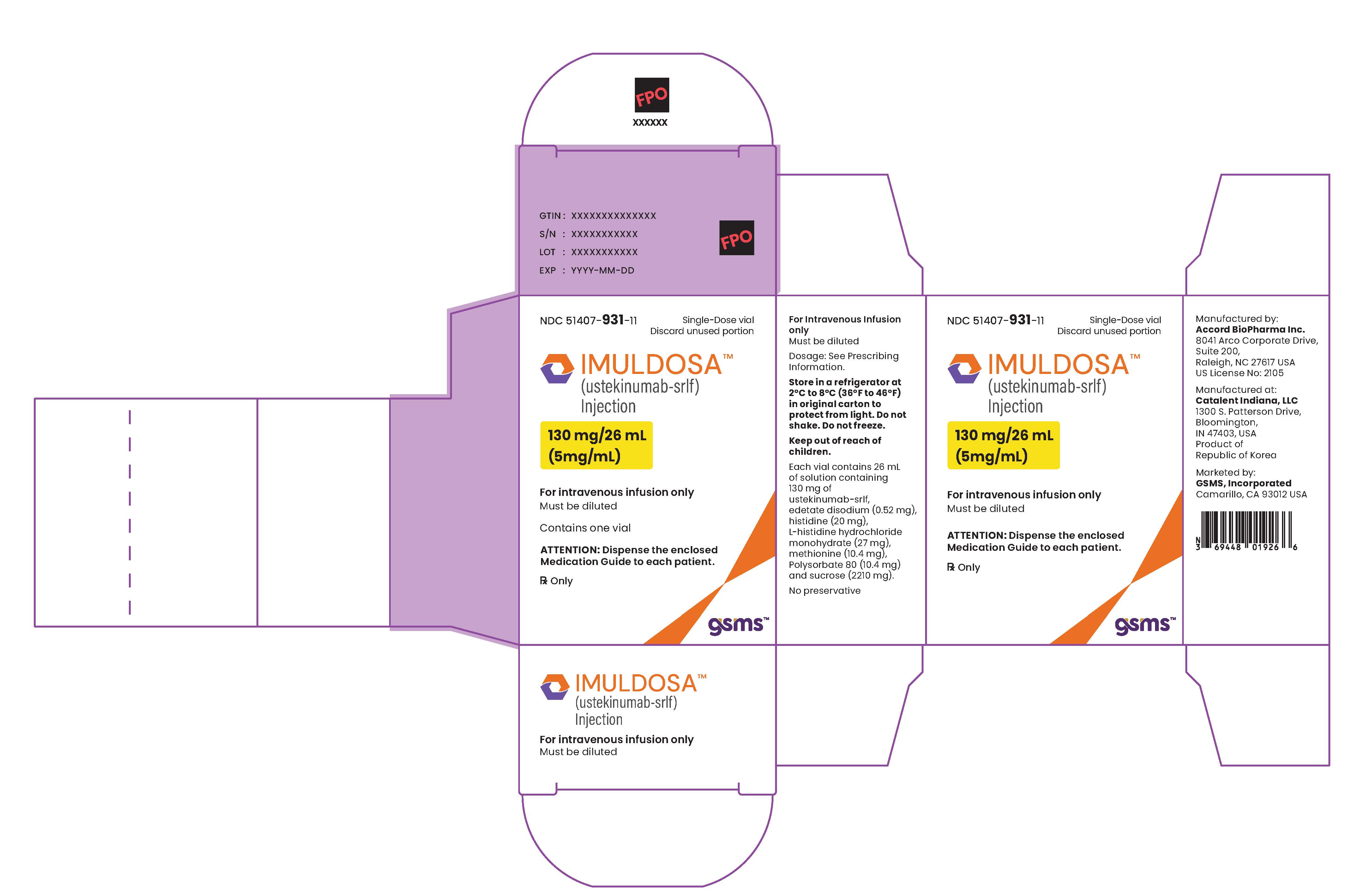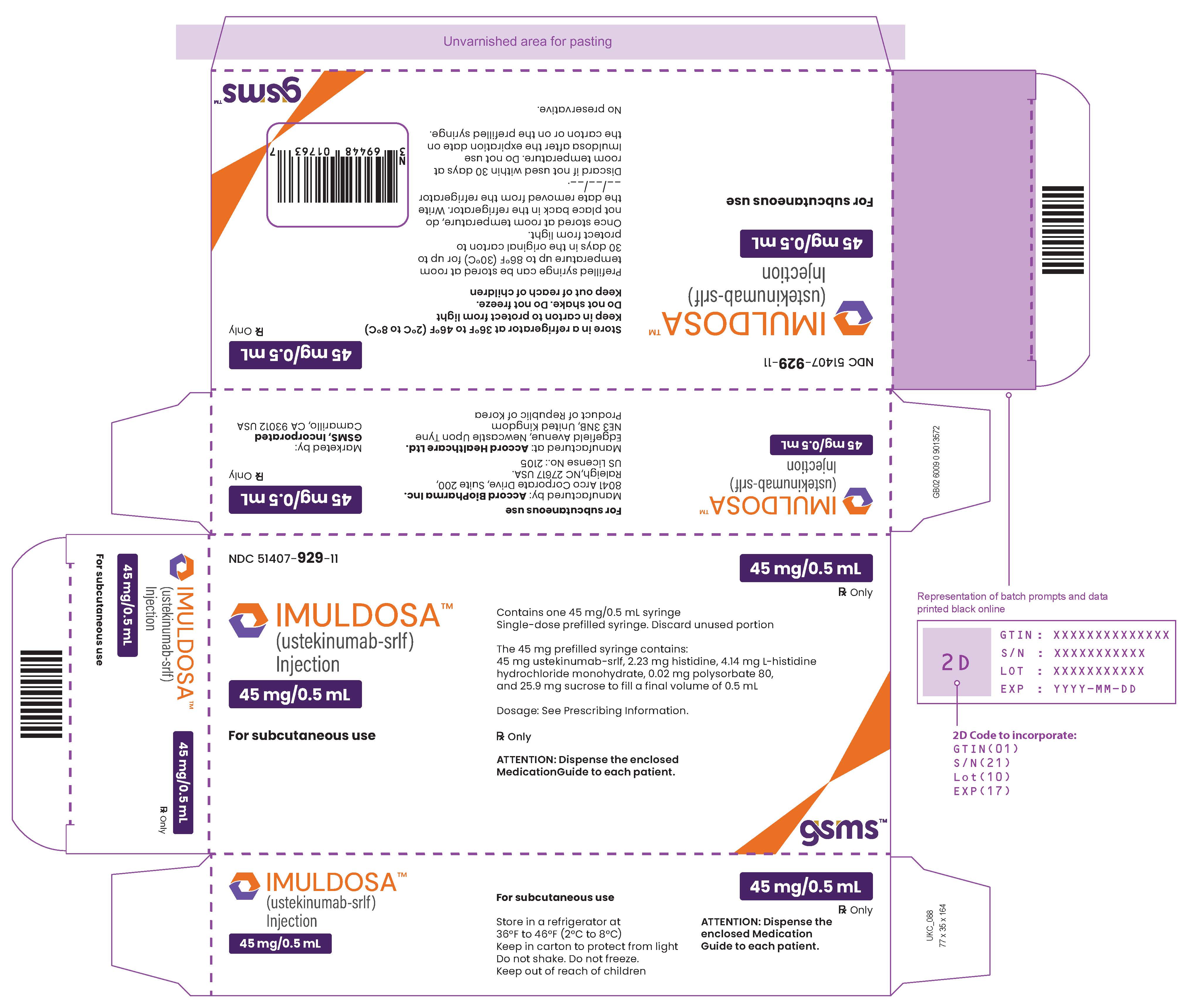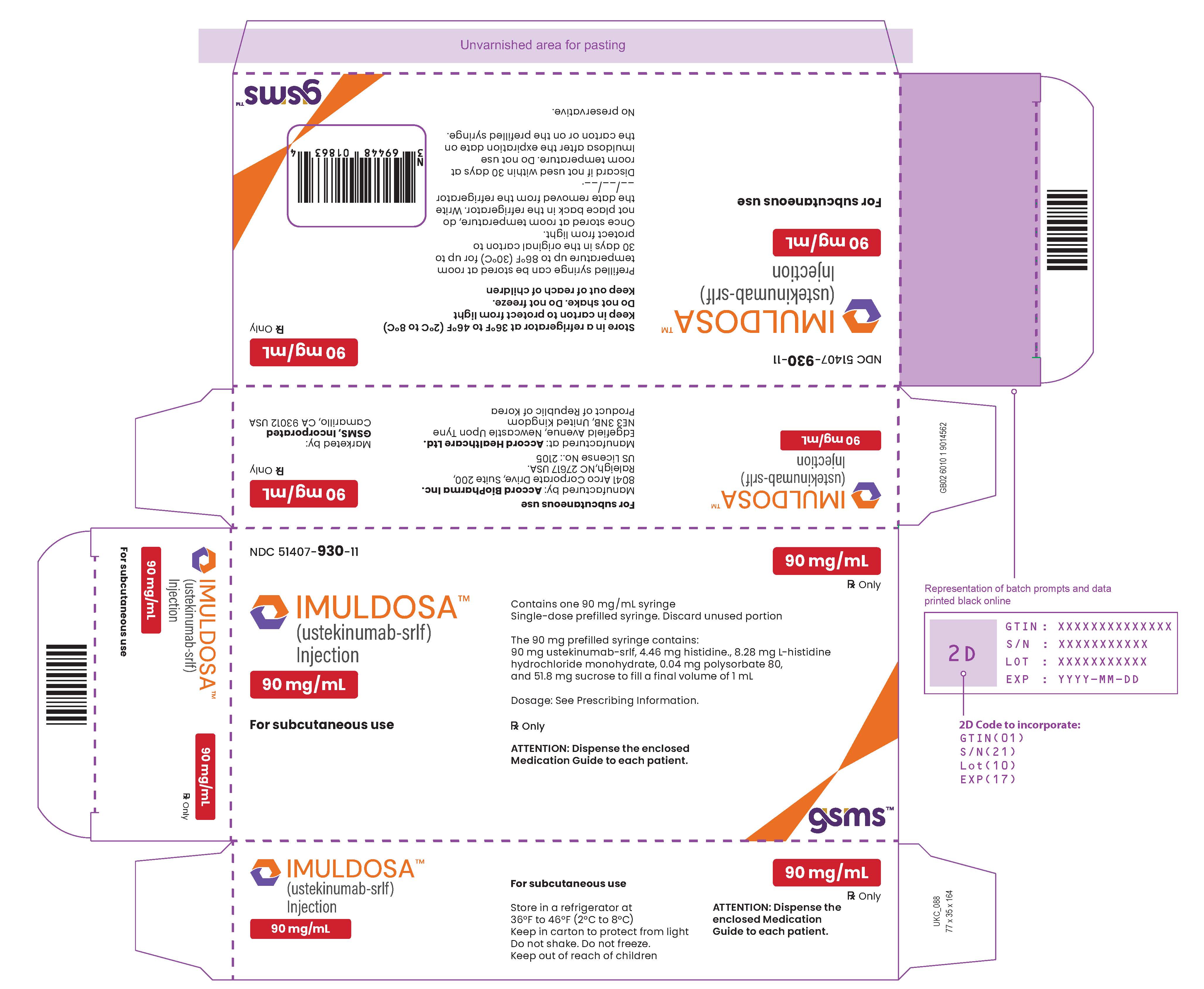 DRUG LABEL: IMULDOSA
NDC: 51407-930 | Form: INJECTION
Manufacturer: Golden State Medical Supply, Inc.
Category: prescription | Type: HUMAN PRESCRIPTION DRUG LABEL
Date: 20260127

ACTIVE INGREDIENTS: USTEKINUMAB-SRLF 90 mg/1 mL
INACTIVE INGREDIENTS: HISTIDINE 4.46 mg/1 mL; HISTIDINE
                                        MONOHYDROCHLORIDE MONOHYDRATE 8.28 mg/1 mL; POLYSORBATE
                                        80 0.04 mg/1 mL; SUCROSE 51.8 mg/1 mL

HIGHLIGHTS OF PRESCRIBING INFORMATION

IMULDOSA. These highlights do not include all the information needed to use IMULDOSA safely and effectively. See full prescribing information for IMULDOSA.
IMULDOSA (ustekinumab-srlf) injection, for subcutaneous or intravenous use
Initial U.S. Approval: 2024
IMULDOSA (ustekinumab-srlf) is biosimilar* to STELARA®(ustekinumab)

1 INDICATIONS AND USAGE

IMULDOSA is a human interleukin-12 and -23 antagonist indicated for the treatment of:
Adult patients with:
• moderate to severe plaque psoriasis (PsO) who are candidates for phototherapy or systemic therapy. (1.1)
• active psoriatic arthritis (PsA). (1.2)
• moderately to severely active Crohn’s disease (CD). (1.3)
• moderately to severely active ulcerative colitis. (1.4)
Pediatric patients 6 years and older with:
• moderate to severe plaque psoriasis (PsO), who are candidates for phototherapy or systemic therapy. (1.1)
• active psoriatic arthritis (PsA). (1.2)

RECENT MAJOR CHANGES

Warnings and Precautions
Serious Hypersensitivity Reactions (5.5) 11/2025

2 DOSAGE AND ADMINISTRATION

Adult Patients with Plaque Psoriasis Subcutaneous Recommended Dosage (2.1):

Weight Range (kilograms) | Dosage Regimen
less than or equal to 100 kg | 45 mg administered subcutaneously initially and 4 weeks later, followed by 45 mg administered subcutaneously every 12 weeks
greater than 100 kg | 90 mg administered subcutaneously initially and 4 weeks later, followed by 90 mg administered subcutaneously every 12 weeks

Pediatric Patients 6 Years of Age and Older with Plaque Psoriasis Subcutaneous Recommended Dosage (2.1): Weight-based dosing is recommended at the initial dose, 4 weeks later, then every 12 weeks thereafter.

Weight Range (kilograms) | Dose
60 kg to 100 kg | 45 mg
greater than 100 kg | 90 mg

Psoriatic Arthritis Adult Subcutaneous Recommended Dosage (2.2):

- The recommended dosage is 45 mg administered subcutaneously initially and 4 weeks later, followed by 45 mg administered subcutaneously every 12 weeks.
- For patients with co-existent moderate-to-severe plaque psoriasis weighing greater than 100 kg, the recommended dosage is 90 mg administered subcutaneously initially and 4 weeks later, followed by 90 mg administered subcutaneously every 12 weeks.

Psoriatic Arthritis Pediatric 6 Years of Age and Older Subcutaneous Recommended Dosage (2.2): Weight-based dosing is recommended at the initial dose, 4 weeks later, then every 12 weeks thereafter.

Weight Range (kilograms) | Dosage Regimen
60 kg or more | 45 mg
greater than 100 kg with co-existent moderate-to-severe plaque psoriasis | 90 mg

Crohn’s Disease and Ulcerative Colitis Initial Adult Intravenous Recommended Dosage (2.3): A single intravenous infusion using weight-based dosing:

Weight Range (kilograms) | Recommended Dosage
up to 55 kg | 260 mg (2 vials)
greater than 55 kg to 85 kg | 390 mg (3 vials)
greater than 85 kg | 520 mg (4 vials)

Crohn’s Disease and Ulcerative Colitis Maintenance Adult Subcutaneous Recommended Dosage (2.3): A subcutaneous 90 mg dose 8 weeks after the initial intravenous dose, then every 8 weeks thereafter.

3 DOSAGE FORMS AND STRENGTHS

Subcutaneous Injection (3)

- Injection: 45 mg/0.5 mL or 90 mg/mL solution in a single-dose prefilled syringe

Intravenous Infusion (3)

- Injection: 130 mg/26 mL (5 mg/mL) solution in a single-dose vial (3)

4 CONTRAINDICATIONS

Clinically significant hypersensitivity to ustekinumab products or to any of the excipients in IMULDOSA

5 WARNINGS AND PRECAUTIONS

- Infections: Serious infections have occurred. Avoid starting IMULDOSA during any clinically important active infection. If a serious infection or clinically significant infection develops, discontinue IMULDOSA until the infection resolves. (5.1)
- Theoretical Risk for Particular Infections: Serious infections from mycobacteria, salmonella and Bacillus Calmette-Guerin (BCG) vaccinations have been reported in patients genetically deficient in IL-12/IL-23. Consider diagnostic tests for these infections as dictated by clinical circumstances. (5.2)
- Tuberculosis (TB): Evaluate patients for TB prior to initiating treatment with IMULDOSA. Initiate treatment of latent TB before administering IMULDOSA. (5.3)
- Malignancies: Ustekinumab products may increase risk of malignancy. The safety of Ustekinumab products in patients with a history of or a known malignancy has not been evaluated. (5.4)
- Serious Hypersensitivity Reactions: If a severe or other clinically significant hypersensitivity reaction occurs, discontinue IMULDOSA immediately and initiate appropriate medical treatment. (5.5)
- Posterior Reversible Encephalopathy Syndrome (PRES): If PRES is suspected, treat promptly and discontinue IMULDOSA. (5.6)
- Immunizations: Avoid use of live vaccines in patients during treatment with IMULDOSA. (5.7)
- Noninfectious Pneumonia: Cases of interstitial pneumonia, eosinophilic pneumonia, and cryptogenic organizing pneumonia have been reported during post-approval use of ustekinumab products. If diagnosis is confirmed, discontinue IMULDOSA and institute appropriate treatment. (5.8)

6 ADVERSE REACTIONS

Most common adverse reactions are:

- Psoriasis and Psoriatic Arthritis (≥3%): nasopharyngitis, upper respiratory tract infection, headache, and fatigue. (6.1)
- Crohn’s Disease, induction (≥3%): vomiting. (6.1)
- Crohn’s Disease, maintenance (≥3%): nasopharyngitis, injection site erythema, vulvovaginal candidiasis/mycotic infection, bronchitis, pruritus, urinary tract infection, and sinusitis. (6.1)
- Ulcerative colitis, induction (≥3%): nasopharyngitis (6.1)
- Ulcerative colitis, maintenance (≥3%): nasopharyngitis, headache, abdominal pain, influenza, fever, diarrhea, sinusitis, fatigue, and nausea (6.1)

To report SUSPECTED ADVERSE REACTIONS, contact Accord BioPharma Inc. at 1-866-941-7875 or FDA at 1-800-FDA-1088 or www.fda.gov/medwatch.

*Biosimilar means that the biological product is approved based on data demonstrating that it is highly similar to an FDA-approved biological product, known as a reference product, and that there are no clinically meaningful differences between the biosimilar product and the reference product. Biosimilarity of IMULDOSA has been demonstrated for the condition(s) of use (e.g., indication(s), dosing regimen(s)), strength(s), dosage form(s), and route(s) of administration described in its Full Prescribing Information.

FULL PRESCRIBING INFORMATION

1 INDICATIONS AND USAGE

1.1 Plaque Psoriasis (PsO)

IMULDOSA is indicated for the treatment of adults and pediatric patients 6 years of age and older with moderate to severe plaque psoriasis who are candidates for phototherapy or systemic therapy.

1.2 Psoriatic Arthritis (PsA)

IMULDOSA is indicated for the treatment of adults and pediatric patients 6 years of age and older with active psoriatic arthritis.

1.3 Crohn’s Disease (CD)

IMULDOSA is indicated for the treatment of adult patients with moderately to severely active Crohn’s disease.

1.4 Ulcerative Colitis

IMULDOSA is indicated for the treatment of adult patients with moderately to severely active ulcerative colitis.

2 DOSAGE AND ADMINISTRATION

2.1 Recommended Dosage in Plaque Psoriasis

Subcutaneous Adult Dosage Regimen

- For patients weighing 100 kg or less, the recommended dosage is 45 mg initially and 4 weeks later, followed by 45 mg every 12 weeks.
- For patients weighing more than 100 kg, the recommended dosage is 90 mg initially and 4 weeks later, followed by 90 mg every 12 weeks.

In subjects weighing more than 100 kg, 45 mg was also shown to be efficacious. However, 90 mg resulted in greater efficacy in these subjects [ see Clinical Studies (14) ].

Subcutaneous Pediatric Dosage Regimen

Administer IMULDOSA subcutaneously at Weeks 0 and 4, then every 12 weeks thereafter.

The recommended dose of IMULDOSA for pediatric patients 6 years of age and older with plaque psoriasis based on body weight is shown below (Table 1).

Table 1: Recommended Dose of IMULDOSA for Subcutaneous Injection in Pediatric Patients 6 years of age and older with Plaque Psoriasis

Body Weight of Patient at the Time of Dosing | Recommended Dose
60 kg to 100 kg | 45 mg
more than 100 kg | 90 mg
There is no dosage form for IMULDOSA that allows weight-based dosing for pediatric patients below 60 kg.

2.2 Recommended Dosage in Psoriatic Arthritis

Subcutaneous Adult Dosage Regimen

- The recommended dosage is 45 mg initially and 4 weeks later, followed by 45 mg every 12 weeks.
- For patients with co-existent moderate-to-severe plaque psoriasis weighing more than 100 kg, the recommended dosage is 90 mg initially and 4 weeks later, followed by 90 mg every 12 weeks.

Subcutaneous Pediatric Dosage Regimen

Administer IMULDOSA subcutaneously at Weeks 0 and 4, then every 12 weeks thereafter.

The recommended dose of IMULDOSA for pediatric patients 6 years of age and older with psoriatic arthritis, based on body weight, is shown below (Table 2).

Table 2: Recommended Dose of IMULDOSA for Subcutaneous Injection in Pediatric Patients 6 years of age and older with Psoriatic Arthritis

Body Weight of Patient at the Time of Dosing | Recommended Dose
60 kg or more | 45 mg
greater than 100 kg with co-existent moderate- to-severe plaque psoriasis | 90 mg

There is no dosage form for IMULDOSA that allows weight-based dosing for pediatric patients below 60 kg.

2.3 Recommended Dosage in Crohn’s Disease and Ulcerative Colitis

Intravenous Induction Adult Dosage Regimen

A single intravenous infusion dose of IMULDOSA using the weight-based dosage regimen specified in Table 3 [ see Instructions for dilution of IMULDOSA 130 mg vial for intravenous infusion (2.5)].

Table 3: Initial Intravenous Dosage of IMULDOSA

Body Weight of Patient at the time of dosing | Dose | Number of 130 mg/26 mL (5 mg/mL) IMULDOSA vials
55 kg or less | 260 mg | 2
more than 55 kg to 85 kg | 390 mg | 3
more than 85 kg | 520 mg | 4

Subcutaneous Maintenance Adult Dosage Regimen

The recommended maintenance dosage is a subcutaneous 90 mg dose administered 8 weeks after the initial intravenous dose, then every 8 weeks thereafter.

2.4 General Considerations for Administration

- IMULDOSA is intended for use under the guidance and supervision of a healthcare provider. IMULDOSA should only be administered to patients who will be closely monitored and have regular follow-up visits with a healthcare provider. The appropriate dose should be determined by a healthcare provider using the patient’s current weight at the time of dosing. In pediatric patients, it is recommended that IMULDOSA be administered by a healthcare provider. If a healthcare provider determines that it is appropriate, a patient may self-inject or a caregiver may inject IMULDOSA after proper training in subcutaneous injection technique. Instruct patients to follow the directions provided in the Instructions for Use [ see Instructions for Use].
- It is recommended that each injection be administered at a different anatomic location (such as upper arms, gluteal regions, thighs, or any quadrant of abdomen) than the previous injection, and not into areas where the skin is tender, bruised, erythematous, or indurated. When using the single-dose vial, a 1 mL syringe with a 27 gauge, ½ inch needle is recommended.
- Prior to administration, visually inspect IMULDOSA for particulate matter and discoloration IMULDOSA is a clear to slightly opalescent and colorless to slightly yellow solution. Do not use IMULDOSA if it is discolored or cloudy, or if other particulate matter is present. IMULDOSA does not contain preservatives; therefore, discard any unused product remaining in the vial and/or syringe.

2.5 Preparation and Administration of IMULDOSA 130 mg/26 mL (5 mg/mL) Vial for Intravenous Infusion (Crohn’s Disease and Ulcerative Colitis)

IMULDOSA solution for intravenous infusion must be diluted, prepared and infused by a healthcare professional using aseptic technique.

1. Calculate the dose and the number of IMULDOSA vials needed based on patient weight (Table 3). Each 26 mL vial of IMULDOSA contains 130 mg of ustekinumab-srlf.
2. Withdraw, and then discard a volume of the 0.9% Sodium Chloride Injection, USP from the 250 mL infusion bag equal to the volume of IMULDOSA to be added (discard 26 mL sodium chloride for each vial of IMULDOSA needed, for 2 vials- discard 52 mL, for 3 vials- discard 78 mL, 4 vials- discard 104 mL). Alternatively, a 250 mL infusion bag containing 0.45% Sodium Chloride Injection, USP may be used. Infusion bags must be made of either polypropylene (PP) or polyethylene (PE).
3. Withdraw 26 mL of IMULDOSA from each vial needed and add it to the 250 mL infusion bag. The final volume in the infusion bag should be 250 mL. Gently mix.
4. Visually inspect the diluted solution before infusion. Do not use if visibly opaque particles, discoloration or foreign particles are observed.
5. Infuse the diluted solution over a period of at least one hour. Once diluted, the infusion should be completely administered within eight hours of the dilution in the infusion bag.
6. Use only an infusion set with an in-line, sterile, non-pyrogenic, low protein-binding filter (pore size 0.2 micrometer).
7. Do not infuse IMULDOSA concomitantly in the same intravenous line with other agents.
8. 8. IMULDOSA does not contain preservatives. Each vial is for one-time use in only one patient. Discard any remaining solution. Dispose any unused medicinal product in accordance with local requirements.

Storage

If necessary, the diluted infusion solution may be kept at room temperature up to 25°C (77°F) for up to 7 hours. Storage time at room temperature begins once the diluted solution has been prepared. The infusion should be completed within 8 hours after the dilution in the infusion bag (cumulative time after preparation including the storage and the infusion period). Do not freeze. Discard any unused portion of the infusion solution.

3 DOSAGE FORMS AND STRENGTHS

IMULDOSA (Ustekinumab-srlf) is a clear to slightly opalescent and colorless to slightly yellow solution.

Subcutaneous Injection

- Injection: 45 mg/0.5 mL or 90 mg/mL solution in a single-dose prefilled syringe

Intravenous Infusion

- Injection: 130 mg/26 mL (5 mg/mL) solution in a single-dose vial

4 CONTRAINDICATIONS

IMULDOSA is contraindicated in patients with clinically significant hypersensitivity to Ustekinumab products or to any of the excipients in IMULDOSA [ see Warnings and Precautions (5.5) ].

5 WARNINGS AND PRECAUTIONS

5.1 Infections

Ustekinumab products may increase the risk of infections and reactivation of latent infections. Serious bacterial, mycobacterial, fungal, and viral infections were observed in patients receiving Ustekinumab products [see Adverse Reactions (6.1, 6.3)] .

Serious infections requiring hospitalization, or otherwise clinically significant infections, reported in clinical trials included the following:

- Plaque Psoriasis: diverticulitis, cellulitis, pneumonia, appendicitis, cholecystitis, sepsis, osteomyelitis, viral infections, gastroenteritis and urinary tract infections.
- Psoriaticarthritis: cholecystitis.
- Crohn’s disease: anal abscess, gastroenteritis, ophthalmic herpes zoster, pneumonia, and listeria meningitis.
- Ulcerative colitis: gastroenteritis, ophthalmic herpes zoster, pneumonia, and listeriosis.

Avoid initiating treatment with IMULDOSA in patients with any clinically important active infection until the infection resolves or is adequately treated. Consider the risks and benefits of treatment prior to initiating use of IMULDOSA in patients with a chronic infection or a history of recurrent infection.

Instruct patients to seek medical advice if signs or symptoms suggestive of an infection occur while on treatment with IMULDOSA and discontinue IMULDOSA for serious or clinically significant infections until the infection resolves or is adequately treated.

5.2 Theoretical Risk for Vulnerability to Particular Infections

Individuals genetically deficient in IL-12/IL-23 are particularly vulnerable to disseminated infections from mycobacteria (including nontuberculous, environmental mycobacteria), salmonella (including nontyphi strains), and Bacillus Calmette-Guerin (BCG) vaccinations. Serious infections and fatal outcomes have been reported in such patients.
It is not known whether patients with pharmacologic blockade of IL-12/IL-23 from treatment with ustekinumab products may be susceptible to these types of infections. Consider appropriate diagnostic testing (e.g., tissue culture, stool culture, as dictated by clinical circumstances).

5.3 Pre-treatment Evaluation for Tuberculosis

Evaluate patients for tuberculosis infection prior to initiating treatment with IMULDOSA.

Avoid administering IMULDOSA to patients with active tuberculosis infection. Initiate treatment of latent tuberculosis prior to administering IMULDOSA. Consider anti-tuberculosis therapy prior to initiation of IMULDOSA in patients with a past history of latent or active tuberculosis in whom an adequate course of treatment cannot be confirmed. Closely monitor patients receiving IMULDOSA for signs and symptoms of active tuberculosis during and after treatment.

5.4 Malignancies

Ustekinumab products are immunosuppressants and may increase the risk of malignancy. Malignancies were reported among subjects who received Ustekinumab in clinical trials [ see Adverse Reactions (6.1) ]. In rodent models, inhibition of IL-12/IL-23p40 increased the risk of malignancy [ see Nonclinical Toxicology (13) ].

The safety of Ustekinumab products has not been evaluated in patients who have a history of malignancy or who have a known malignancy.
There have been post-marketing reports of the rapid appearance of multiple cutaneous squamous cell carcinomas in patients receiving ustekinumab products who had pre-existing risk factors for developing non-melanoma skin cancer. Monitor all patients receiving IMULDOSA for the appearance of non-melanoma skin cancer. Closely follow patients greater than 60 years of age, those with a medical history of prolonged immunosuppressant therapy and those with a history of PUVA treatment [ see Adverse Reactions (6.1) ].

5.5 Serious Hypersensitivity Reactions

Serious hypersensitivity reactions, including anaphylaxis and angioedema, have been reported with ustekinumab products in clinical trials and postmarketing. Some serious hypersensitivity reactions have occurred during the first intravenous dose of ustekinumab products [ see Adverse Reactions(6.1, 6.3)]. If a severe or clinically significant hypersensitivity reaction occurs, discontinue IMULDOSA immediately and initiate appropriate medical treatment [ see Contraindications (4) ].

5.6 Posterior Reversible Encephalopathy Syndrome (PRES)

Two cases of posterior reversible encephalopathy syndrome (PRES), also known as Reversible Posterior Leukoencephalopathy Syndrome (RPLS), were reported in clinical trials. Cases have also been reported in postmarketing experience in patients with psoriasis, psoriatic arthritis, and Crohn’s disease. Clinical presentation included headaches, seizures, confusion, visual disturbances, and imaging changes consistent with PRES a few days to several months after ustekinumab product initiation. A few cases reported latency of a year or longer. Patients recovered with supportive care following withdrawal of ustekinumab products.

Monitor all patients treated with IMULDOSA for signs and symptoms of PRES. If PRES is suspected, promptly administer appropriate treatment, and discontinue IMULDOSA.

5.7 Immunizations

Prior to initiating therapy with IMULDOSA, patients should receive all age-appropriate immunizations as recommended by current immunization guidelines. Patients being treated with IMULDOSA should avoid receiving live vaccines. Avoid administering BCG vaccines during treatment with IMULDOSA or for one year prior to initiating treatment or one year following discontinuation of treatment. Caution is advised when administering live vaccines to household contacts of patients receiving IMULDOSA because of the potential risk for shedding from the household contact and transmission to patient.

Non-live vaccinations received during a course of IMULDOSA may not elicit an immune response sufficient to prevent disease.

5.8 Noninfectious Pneumonia

Cases of interstitial pneumonia, eosinophilic pneumonia, and cryptogenic organizing pneumonia have been reported during post-approval use of ustekinumab products. Clinical presentations included cough, dyspnea, and interstitial infiltrates following one to three doses. Serious outcomes have included respiratory failure and prolonged hospitalization. Patients improved with discontinuation of therapy and in certain cases administration of corticosteroids. If diagnosis is confirmed, discontinue IMULDOSA and institute appropriate treatment [ see Postmarketing Experience (6.3) ].

6 ADVERSE REACTIONS

The following serious adverse reactions are discussed elsewhere in the label:

- Infections [see Warnings and Precautions (5.1)]
- Malignancies [see Warnings and Precautions (5.4)]
- Serious Hypersensitivity Reactions [see Warnings and Precautions (5.5)]
- Posterior Reversible Encephalopathy Syndrome (PRES) [see Warnings and Precautions (5.6)]
- Noninfectious Pneumonia [see Warnings and Precautions (5.8)]

6.1 Clinical Trials Experience

Because clinical trials are conducted under widely varying conditions, adverse reaction rates observed in the clinical trials of a drug cannot be directly compared to rates in the clinical trials of another drug and may not reflect the rates observed in practice.

Adult Subjects with Plaque Psoriasis
The safety data reflect exposure to Ustekinumab in 3117 adult subjects with plaque psoriasis, including 2414 exposed for at least 6 months, 1855 exposed for at least one year, 1653 exposed for at least two years, 1569 exposed for at least three years, 1482 exposed for at least four years and 838 exposed for at least five years.
Table 4 summarizes the adverse reactions that occurred at a rate of at least 1% with higher rates in the Ustekinumab groups during the placebo-controlled period of Ps STUDY 1 and Ps STUDY 2 [ see Clinical Studies(14)].

Table 4: Adverse Reactions, Reported by ≥1% of Subjects with Plaque Psoriasis and at Higher Rates in the Ustekinumab groups through Week 12 in Ps STUDY 1 and Ps STUDY 2

 |  | Ustekinumab
 | Placebo | 45 mg | 90 mg
Subjects treated | 665 | 664 | 666
Nasopharyngitis | 51 (8%) | 56 (8%) | 49 (7%)
Upper respiratory tract infection | 30 (5%) | 36 (5%) | 28 (4%)
Headache | 23 (3%) | 33 (5%) | 32 (5%)
Fatigue | 14 (2%) | 18 (3%) | 17 (3%)
Back pain | 8 (1%) | 9 (1%) | 14 (2%)
Dizziness | 8 (1%) | 8 (1%) | 14 (2%)
Pharyngolaryngeal pain | 7 (1%) | 9 (1%) | 12 (2%)
Pruritus | 9 (1%) | 10 (2%) | 9 (1%)
Injection site erythema | 3 (<1%) | 6 (1%) | 13 (2%)
Myalgia | 4 (1%) | 7 (1%) | 8 (1%)
Depression | 3 (<1%) | 8 (1%) | 4 (1%)

Adverse reactions that occurred at rates less than 1% in the controlled period of Ps STUDIES 1 and 2 through week 12 included: cellulitis, herpes zoster, diverticulitis and certain injection site reactions (pain, swelling, pruritus, induration, hemorrhage, bruising, and irritation).
One case of PRES occurred during clinical trials in adult subjects with plaque psoriasis [ see Warnings and Precautions(5.6)].

Infections
In the placebo-controlled period of clinical trials of subjects with plaque psoriasis (average follow-up of 12.6 weeks for subjects receiving placebo and 13.4 weeks for Ustekinumab-treated subjects), 27% of Ustekinumab-treated subjects reported infections (1.39 per patient-years of follow-up) compared with 24% of subjects receiving placebo (1.21 per patient-years of follow-up). Serious infections occurred in 0.3% of ustekinumab-treated subjects (0.01 per patient-years of follow-up) and in 0.4% of subjects receiving placebo (0.02 per patient-years of follow-up) [ see Warnings and Precautions(5.1)].
In the controlled and non-controlled portions of clinical trials in subjects with plaque psoriasis (median follow-up of 3.2 years), representing 8998 patient-years of exposure, 72.3% of Ustekinumab- treated subjects reported infections (0.87 per patient-years of follow-up). Serious infections were reported in 2.8% of subjects (0.01 per patient-years of follow-up).

Malignancies
In the controlled and non-controlled portions of clinical trials in subjects with plaque psoriasis (median follow-up of 3.2 years, representing 8998 patient-years of exposure), 1.7% of ustekinumab-treated subjects reported malignancies excluding non-melanoma skin cancers (0.60 per hundred patient-years of follow-up). Non-melanoma skin cancer was reported in 1.5% of ustekinumab-treated subjects (0.52 per hundred patient-years of follow-up) [ see Warnings and Precautions(5.4)]. The most frequently observed malignancies other than non-melanoma skin cancer during the clinical trials were: prostate, melanoma, colorectal and breast. Malignancies other than non-melanoma skin cancer in ustekinumab-treated subjects during the controlled and uncontrolled portions of trials were similar in type and number to what would be expected in the general U.S. population according to the SEER database (adjusted for age, gender and race).^1

Pediatric Subjects with Plaque Psoriasis
The safety of ustekinumab was assessed in two trials of pediatric subjects with moderate to severe plaque psoriasis. Ps STUDY 3 evaluated safety for up to 60 weeks in 110 pediatric subjects 12 to 17 years old. Ps STUDY 4 evaluated safety for up to 56 weeks in 44 pediatric subjects 6 to 11 years old. The safety profile in pediatric subjects was similar to the safety profile from trials in adults with plaque psoriasis.

Psoriatic Arthritis
The safety of ustekinumab was assessed in 927 subjects in two randomized, double- blind, placebo-controlled trials in adults with active psoriatic arthritis (PsA). The overall safety profile of ustekinumab in subjects with PsA was consistent with the safety profile seen in clinical trials in adult subjects with plaque psoriasis . A higher incidence of arthralgia, nausea, and dental infections was observed in ustekinumab-treated subjects when compared with placebo-treated subjects (3% vs. 1% for arthralgia and 3% vs. 1% for nausea; 1% vs. 0.6% for dental infections) in the placebo- controlled portions of the PsA clinical trials.

Crohn’s Disease
The safety of ustekinumab was assessed in 1407 subjects with moderately to severely active Crohn’s disease (Crohn’s Disease Activity Index [CDAI] greater than or equal to 220 and less than or equal to 450) in three randomized, double- blind, placebo-controlled, parallel-group, multicenter trials. These 1407 subjects included 40 subjects who received a prior investigational intravenous ustekinumab formulation but were not included in the efficacy analyses. In trials CD-1 and CD-2 there were 470 subjects who received ustekinumab 6 mg/kg as a weight-based single intravenous induction dose and 466 who received placebo [ see Dosage and Administration(2.3)]. Subjects who were responders in either trial CD-1 or CD-2 were randomized to receive a subcutaneous maintenance regimen of either 90 mg ustekinumab every 8 weeks, or placebo for 44 weeks in trial CD-3. Subjects in these 3 trials may have received other concomitant therapies including aminosalicylates, immunomodulatory agents [azathioprine (AZA), 6-mercaptopurine (6-MP), methotrexate (MTX)], oral corticosteroids (prednisone or budesonide), and/or antibiotics for their Crohn’s disease [ see Clinical Studies (14.4) ].
The overall safety profile of ustekinumab was consistent with the safety profile seen in the clinical trials in adult subjects with plaque psoriasis and psoriatic arthritis. Common adverse reactions in trials CD-1 and CD-2 and in trial CD-3 are listed in Tables 5 and 6, respectively.

Table 5:Common adverse reactions through Week 8 in trials CD-1 and CD-2 occurring in ≥3% of ustekinumab-treated subjects and higher than subjects receiving placebo

 | Placebo N=466 | Ustekinumab 6 mg/kg single intravenous induction dose N=470
Vomiting | 3% | 4%

Other less common adverse reactions reported in subjects in trials CD-1 and CD-2 included asthenia (1% vs 0.4%), acne (1% vs 0.4%), and pruritus (2% vs 0.4%).

Table 6: Common adverse reactions through Week 44 in trial CD-3 occurring in ≥3% of ustekinumab-treated subjects and higher than subjects receiving placebo

 | Placebo N=133 | Ustekinumab 90 mg subcutaneous maintenance dose every 8 weeks N=131
Nasopharyngitis | 8% | 11%
Injection site erythema | 0 | 5%
Vulvovaginal candidiasis/mycotic infection | 1% | 5%
Bronchitis | 3% | 5%
Pruritus | 2% | 4%
Urinary tract infection | 2% | 4%
Sinusitis | 2% | 3%

Infections
In subjects with Crohn’s disease, serious or other clinically significant infections included anal abscess, gastroenteritis, and pneumonia. In addition, listeria meningitis and ophthalmic herpes zoster were reported in one subject each [see Warnings and Precautions (5.1)].

Malignancies
With up to one year of treatment in the Crohn’s disease clinical trials, 0.2% of ustekinumab-treated subjects (0.36 events per hundred patient-years) and 0.2% of placebo-treated subjects (0.58 events per hundred patient-years) developed non- melanoma skin cancer. Malignancies other than non-melanoma skin cancers occurred in 0.2% of ustekinumab-treated subjects (0.27 events per hundred patient- years) and in none of the placebo-treated subjects.

Hypersensitivity Reactions Including Anaphylaxis
In CD trials, two subjects reported hypersensitivity reactions following ustekinumab administration. One subject experienced signs and symptoms consistent with anaphylaxis (tightness of the throat, shortness of breath, and flushing) after a single subcutaneous administration (0.1% of subjects receiving subcutaneous ustekinumab). In addition, one subject experienced signs and symptoms consistent with or related to a hypersensitivity reaction (chest discomfort, flushing, urticaria, and increased body temperature) after the initial intravenous ustekinumab dose (0.08% of subjects receiving intravenous ustekinumab). These subjects were treated with oral antihistamines or corticosteroids and in both cases symptoms resolved within an hour [see Warnings and Precautions (5.5)].

Ulcerative Colitis
The safety of ustekinumab was evaluated in two randomized, double-blind, placebo- controlled clinical trials (UC-1 [IV induction] and UC-2 [SC maintenance]) in 960 adult subjects with moderately to severely active ulcerative colitis [ see Clinical Studies (14.5) ]. The overall safety profile of ustekinumab in subjects with ulcerative colitis was consistent with the safety profile seen across all approved indications. Adverse reactions reported in at least 3% of ustekinumab-treated subjects and at a higher rate than placebo were:
• Induction (UC-1): nasopharyngitis (7% vs 4%).
• Maintenance (UC-2): nasopharyngitis (24% vs 20%), headache (10% vs 4%), abdominal pain (7% vs 3%), influenza (6% vs 5%), fever (5% vs. 4%), diarrhea (4% vs 1%), sinusitis (4% vs 1%), fatigue (4% vs 2%), and nausea (3% vs 2%).

Infections
In subjects with ulcerative colitis, serious or other clinically significant infections included gastroenteritis and pneumonia. In addition, listeriosis and ophthalmic herpes zoster were reported in one subject each [ see Warnings and Precautions (5.1) ].

Malignancies
With up to one year of treatment in the ulcerative colitis clinical trials, 0.4% of ustekinumab-treated subjects (0.48 events per hundred patient-years) and 0.0% of subjects receiving placebo (0.00 events per hundred patient-years) developed non-melanoma skin cancer. Malignancies other than non-melanoma skin cancers occurred in 0.5% of ustekinumab-treated subjects (0.64 events per hundred patient- years) and 0.2% of subjects receiving placebo (0.40 events per hundred patient-years).

6.2 Immunogenicity

The observed incidence of anti-drug antibodies is highly dependent on the sensitivity and specificity of the assay. Differences in assay methods preclude meaningful comparisons of the incidence of anti-drug antibodies in the studies described below with the incidence of anti-drug antibodies in other studies, including those of ustekinumab or of other ustekinumab products.

Approximately 6 to 12.4% of subjects treated with ustekinumab in clinical trials in subjects with plaque psoriasis and psoriatic arthritis developed antibodies to ustekinumab, which were generally low-titer. In clinical trials in subjects with plaque psoriasis, antibodies to ustekinumab were associated with reduced or undetectable serum ustekinumab concentrations and reduced efficacy. In trials in subjects with plaque psoriasis, the majority of subjects who were positive for antibodies to ustekinumab had neutralizing antibodies.

In clinical trials in subjects with Crohn’s disease and ulcerative colitis, 2.9% and 4.6% of subjects, respectively, developed antibodies to ustekinumab when treated with ustekinumab for approximately one year. No apparent association between the development of antibodies to ustekinumab and the development of injection site reactions was seen.

6.3 Postmarketing Experience

The following adverse reactions have been reported during post-approval use of ustekinumab products. Because these reactions are reported voluntarily from a population of uncertain size, it is not always possible to reliably estimate their frequency or establish a causal relationship to ustekinumab product exposure.

Immune system disorders:Hypersensitivity reactions (e.g., anaphylaxis, angioedema, dyspnea, rash, urticaria), including a fatal case that presented with chest tightness and dyspnea during infusion of the first dose.

Infections and infestations:Lower respiratory tract infection (including opportunistic fungal infections and tuberculosis).

Neurological disorders:Posterior Reversible Encephalopathy Syndrome (PRES).

Respiratory, thoracic and mediastinal disorders:Interstitial pneumonia, eosinophilic pneumonia and cryptogenic organizing pneumonia.

Skin reactions:Pustular psoriasis, erythrodermic psoriasis, hypersensitivity vasculitis.

7 DRUG INTERACTIONS

7.1 Concomitant Therapies

In trials in subjects with plaque psoriasis, the safety of ustekinumab products in combination with immunosuppressive agents or phototherapy has not been evaluated. In trials in subjects with psoriatic arthritis, concomitant MTX use did not appear to influence the safety or efficacy of ustekinumab. In trials in subjects with Crohn’s disease (CD-1 and CD-2) and ulcerative colitis (UC-1), immunomodulators (6-MP, AZA, MTX) were used concomitantly in approximately 30% of subjects and corticosteroids were used concomitantly in approximately 40% and 50% of Crohn’s disease and ulcerative colitis subjects, respectively. Use of these concomitant therapies did not appear to influence the overall safety or efficacy of ustekinumab.

7.2 CYP450 Substrates

The formation of CYP450 enzymes can be suppressed by increased levels of certain cytokines (e.g., IL-1, IL-6, TNFα, IFN) during chronic inflammation. Thus, use of ustekinumab products, antagonists of IL-12 and IL-23, could normalize the formation of CYP450 enzymes. Upon initiation or discontinuation of IMULDOSA in patients who are receiving concomitant CYP450 substrates, particularly those with a narrow therapeutic index, consider monitoring for therapeutic effect or drug concentration and adjust the individual dosage of the CYP substrate as needed. See the prescribing information of specific CYP substrates.
A CYP-mediated drug interaction effect was not observed in subjects with Crohn’s disease [see Clinical Pharmacology (12.3)] .

7.3 Allergen Immunotherapy

Ustekinumab products have not been evaluated in patients who have undergone allergy immunotherapy. Ustekinumab products may decrease the protective effect of allergen immunotherapy (decrease tolerance) which may increase the risk of an allergic reaction to a dose of allergen immunotherapy. Therefore, caution should be exercised in patients receiving or who have received allergen immunotherapy, particularly for anaphylaxis.

8 USE IN SPECIFIC POPULATIONS

8.1 Pregnancy

Risk Summary

Available data from the Organization of Teratology Information Specialists (OTIS)/MotherToBaby Pregnancy Registry, published literature and pharmacovigilance in pregnant women have not identified a ustekinumab- associated risk of major birth defects, miscarriage or other adverse maternal or fetal outcomes (see Data). There are risks to the mother and the fetus associated with inflammatory bowel disease (IBD) in pregnancy. In animal reproductive and developmental toxicity studies, no adverse developmental effects were observed in offspring after administration of ustekinumab to pregnant monkeys at exposures greater than 100 times the maximum recommended human dose (MRHD).
All pregnancies have a background risk of birth defect, loss, or other adverse outcomes. In the U.S. general population, the estimated background risk of major birth defects and miscarriage of clinically recognized pregnancies is 2% to 4% and 15% to 20%, respectively.

Clinical Considerations

Disease-associated Maternal and Embryo/Fetal Risk

Published data suggest that the risk of adverse pregnancy outcomes in women with IBD is associated with increased disease activity. Adverse pregnancy outcomes include preterm delivery (before 37 weeks of gestation), low birth weight (less than 2500 g) infants, and small for gestational age at birth.

Fetal/Neonatal Adverse Reactions

Transport of endogenous IgG antibodies across the placenta increases as pregnancy progresses, and peaks during the third trimester. Therefore, ustekinumab products may be present in infants exposed in utero. The potential clinical impact of ustekinumab product exposure in infants exposed in utero should be considered.

Data

Human Data

An observational pregnancy registry conducted by (OTIS)/MotherToBaby in the U.S. and Canada (enrollment between 2013 and 2019) assessed the risk of major birth defects, pattern of major and minor anomalies in live-born infants, miscarriage, and adverse infant outcomes in women with ustekinumab exposure. In the registry study, there were 101 participants and 107 pregnancies with exposure to ustekinumab (88 prospective; 19 retrospective). Most participants had a primary indication of CD (65.4%) or psoriasis (30.8%). The pregnancy registry did not identify a ustekinumab-associated risk of major birth defects, pattern of major or minor anomalies, increased risk of miscarriage or adverse infant outcomes. Methodological limitations of the registry include small sample size, lack of an internal comparison group, a mix of prospective and retrospective reports, and unmeasured confounders. The conclusions from the pregnancy registry were consistent with the published literature and pharmacovigilance.

Animal Data

Ustekinumab was tested in two embryo-fetal development toxicity studies in cynomolgus monkeys. No teratogenic or other adverse developmental effects were observed in fetuses from pregnant monkeys that were administered ustekinumab subcutaneously twice weekly or intravenously weekly during the period of organogenesis. Serum concentrations of ustekinumab in pregnant monkeys were greater than 100 times the serum concentration in patients treated subcutaneously with 90 mg of ustekinumab weekly for 4 weeks.
In a combined embryo-fetal development and pre- and post-natal development toxicity study, pregnant cynomolgus monkeys were administered subcutaneous doses of ustekinumab twice weekly at exposures greater than 100 times the MRHD from the beginning of organogenesis to Day 33 after delivery. Neonatal deaths occurred in the offspring of one monkey administered ustekinumab at 22.5 mg/kg and one monkey dosed at 45 mg/kg. No ustekinumab- related effects on functional, morphological, or immunological development were observed in the neonates from birth through six months of age.

8.2 Lactation

Risk Summary
Limited data from published literature suggests that ustekinumab is present in human breast milk. There are no available data on the effects of ustekinumab products on milk production. The effects of local gastrointestinal exposure and limited systemic exposure in the breastfed infant to ustekinumab products are unknown. No adverse effects on the breastfed infant causally related to ustekinumab products have been identified in the published literature or postmarketing experience.

The developmental and health benefits of breastfeeding should be considered along with the mother’s clinical need for IMULDOSA and any potential adverse effects on the breastfed child from IMULDOSA or from the underlying maternal condition.

8.4 Pediatric Use

Plaque Psoriasis
The safety and effectiveness of IMULDOSA have been established for the treatment of moderate to severe plaque psoriasis in pediatric patients 6 years of age and older who are candidates for phototherapy or systemic therapy.

Use of IMULDOSA in pediatric patients 12 to less than 17 years of age is supported by evidence from a multicenter, randomized, 60-week trial (Ps STUDY 3) of ustekinumab that included a 12 week, double-blind, placebo-controlled, parallel-group portion, in 110 pediatric subjects 12 years of age and older [see Adverse Reactions (6.1), Clinical Studies (14.2)] .
Use of IMULDOSA in pediatric patients 6 to 11 years of age is supported by evidence from an open-label, single-arm, efficacy, safety and pharmacokinetics trial (Ps STUDY 4) of ustekinumab in 44 subjects [see Adverse Reactions (6.1), Pharmacokinetics (12.3)] .
The safety and effectiveness of IMULDOSA have not been established in pediatric patients less than 6 years of age with plaque psoriasis.

Psoriatic Arthritis
The safety and effectiveness of IMULDOSA have been established for treatment of psoriatic arthritis in pediatric patients 6 years of age and older.
Use of IMULDOSA in these age groups is supported by evidence from adequate and well controlled trials of ustekinumab in adult subjects with psoriasis and PsA, pharmacokinetic data from adult subjects with psoriasis, adult subjects with PsA and pediatric subjects with psoriasis, and safety data of ustekinumab from two clinical trials in 44 pediatric subjects 6 to 11 years old with psoriasis and 110 pediatric subjects 12 years of age and older with psoriasis. The observed pre-dose (trough) concentrations are generally comparable between adult subjects with psoriasis, adult subjects with PsA and pediatric subjects with psoriasis, and the PK exposure is expected to be comparable between adult and pediatric subjects with PsA [see Adverse Reactions (6.1), Clinical Pharmacology (12.3), and Clinical Studies (14.1, 14.2, 14.3)] .
The safety and effectiveness of IMULDOSA have not been established in pediatric patients less than 6 years old with psoriatic arthritis.

Crohn’s Disease and Ulcerative Colitis
The safety and effectiveness of IMULDOSA have not been established in pediatric patients with Crohn’s disease or ulcerative colitis.

8.5 Geriatric Use

Of the 6709 subjects exposed to ustekinumab, a total of 340 were 65 years of age or older (183 subjects with plaque psoriasis, 65 subjects with psoriatic arthritis, 58 subjects with Crohn’s disease and 34 subjects with ulcerative colitis), and 40 subjects were 75 years of age or older. Clinical trials of ustekinumab did not include sufficient numbers of subjects 65 years of age and older to determine whether they respond differently from younger adult subjects.

10 OVERDOSAGE

Single doses up to 6 mg/kg intravenously have been administered in clinical trials without dose-limiting toxicity. In case of overdosage, monitor the patient for any signs or symptoms of adverse reactions or effects and institute appropriate symptomatic treatment immediately.

Consider contacting the Poison Help line (1-800-222-1222) or a medical toxicologist for additional overdose management recommendations.

11 DESCRIPTION

Ustekinumab-srlf, a human IgG1κ monoclonal antibody, is a human interleukin-12 and -23 antagonist. Using DNA recombinant technology, ustekinumab-srlf is produced in a murine cell line (Sp2/0). The manufacturing process contains steps for the clearance of viruses. Ustekinumab-srlf is comprised of 1326 amino acids and has an estimated molecular mass that ranges from 148,079 to 149,690 Daltons.

IMULDOSA (ustekinumab-srlf) injection is a sterile, preservative-free, clear to slightly opalescent and colorless to slightly yellow solution with pH of 5.7- 6.3.

IMULDOSA for Subcutaneous Use
Available as 45 mg of ustekinumab-srlf in 0.5 mL and 90 mg of ustekinumab-srlf in 1 mL, supplied as a sterile solution in a single-dose prefilled syringe with a 29-gauge fixed ½ inch needle. The syringe is fitted with a passive needle guard and a needle cover that does not contains latex.

Each 0.5 mL prefilled syringe delivers 45 mg ustekinumab-srlf, histidine (2.23 mg) and L-histidine hydrochloride monohydrate (4.14 mg), polysorbate 80 (0.02 mg), and sucrose (25.9 mg).

Each 1 mL prefilled syringe delivers 90 mg ustekinumab-srlf, histidine (4.46 mg) and L-histidine hydrochloride monohydrate (8.28 mg), polysorbate 80 (0.04 mg), and sucrose (51.8 mg).

IMULDOSA for Intravenous Infusion
Available as 130 mg of ustekinumab-srlf in 26 mL, supplied as a single-dose 30 mL Type I glass vial with a coated stopper.

Each 26 mL vial delivers 130 mg ustekinumab-srlf, edetate disodium (0.52 mg), histidine (20 mg), L-histidine hydrochloride monohydrate (27 mg), methionine (10.4 mg), Polysorbate 80 (10.4 mg) and sucrose (2,210 mg).

12 CLINICAL PHARMACOLOGY

12.1 Mechanism of Action

Ustekinumab products are human IgG1κ monoclonal antibodies that bind with specificity to the p40 protein subunit used by both the IL-12 and IL-23 cytokines. IL-12 and IL-23 are naturally occurring cytokines that are involved in inflammatory and immune responses, such as natural killer cell activation and CD4+ T-cell differentiation and activation. In in vitro models, ustekinumab products were shown to disrupt IL-12 and IL-23 mediated signaling and cytokine cascades by disrupting the interaction of these cytokines with a shared cell-surface receptor chain, IL-12Rβ1. The cytokines IL-12 and IL-23 have been implicated as important contributors to the chronic inflammation that is a hallmark of Crohn’s disease and ulcerative colitis. In animal models of colitis, genetic absence or antibody blockade of the p40 subunit of IL-12 and IL-23, the target of ustekinumab products, was shown to be protective.

12.2 Pharmacodynamics

Plaque Psoriasis
In a small exploratory trial, a decrease was observed in the expression of mRNA of its molecular targets IL-12 and IL-23 in lesional skin biopsies measured at baseline and up to two weeks post-treatment in subjects with plaque psoriasis.

Ulcerative Colitis
In both trial UC-1 (induction) and trial UC-2 (maintenance), a positive relationship was observed between exposure and rates of clinical remission, clinical response, and endoscopic improvement. The response rate approached a plateau at the ustekinumab exposures associated with the recommended dosing regimen for maintenance treatment [ see Clinical Studies(14.5)].

12.3 Pharmacokinetics

Absorption
In adult subjects with plaque psoriasis, the median time to reach the maximum serum concentration (Tmax) was 13.5 days and 7 days, respectively, after a single subcutaneous administration of 45 mg (N=22) and 90 mg (N=24) of ustekinumab. In healthy subjects (N=30), the median Tmaxvalue (8.5 days) following a single subcutaneous administration of 90 mg of ustekinumab was comparable to that observed in subjects with plaque psoriasis.

Following multiple subcutaneous doses of ustekinumab in adult subjects with plaque psoriasis, steady-state serum concentrations of ustekinumab were achieved by Week 28. The mean (±SD) steady-state trough serum ustekinumab concentrations were 0.69 ± 0.69 mcg/mL for subjects less than or equal to 100 kg receiving a 45 mg dose and 0.74 ± 0.78 mcg/mL for subjects greater than 100 kg receiving a 90 mg dose. There was no apparent accumulation in serum ustekinumab concentration over time when given subcutaneously every 12 weeks.

Following the recommended intravenous induction dose, mean ±SD peak serum ustekinumab concentration was 125.2 ± 33.6 mcg/mL in subjects with Crohn’s disease, and 129.1 ± 27.6 mcg/mL in subjects with ulcerative colitis. Starting at Week 8, the recommended subcutaneous maintenance dosing of 90 mg ustekinumab was administered every 8 weeks. Steady state ustekinumab concentration was achieved by the start of the second maintenance dose. There was no apparent accumulation in ustekinumab concentration over time when given subcutaneously every 8 weeks. Mean ±SD steady-state trough concentration was 2.5 ± 2.1 mcg/mL in subjects with Crohn’s disease, and 3.3 ± 2.3 mcg/mL in subjects with ulcerative colitis for 90 mg ustekinumab administered every 8 weeks.

Distribution
Population pharmacokinetic analyses showed that the volume of distribution of ustekinumab in the central compartment was 2.7 L (95% CI: 2.69, 2.78) in subjects with Crohn’s disease and 3.0 L (95% CI: 2.96, 3.07) in subjects with ulcerative colitis. The total volume of distribution at steady-state was 4.6 L in subjects with Crohn’s disease and 4.4 L in subjects with ulcerative colitis.

Elimination
The mean (±SD) half-life ranged from 14.9 ± 4.6 to 45.6 ± 80.2 days across all trials in subjects with plaque psoriasis following subcutaneous administration. Population pharmacokinetic analyses showed that the clearance of ustekinumab was 0.19 L/day (95% CI: 0.185, 0.197) in subjects with Crohn’s disease and 0.19 L/day (95% CI: 0.179, 0.192) in subjects with ulcerative colitis with an estimated median terminal half-life of approximately 19 days for both IBD (Crohn’s disease and ulcerative colitis) populations.
These results indicate the pharmacokinetics of ustekinumab were similar between subjects with Crohn’s disease and ulcerative colitis.

Metabolism
The metabolic pathway of ustekinumab products has not been characterized. As a human IgG1κ monoclonal antibody, ustekinumab products are expected to be degraded into small peptides and amino acids via catabolic pathways in the same manner as endogenous IgG.

Specific Populations

WeightWhen given the same dose, subjects with plaque psoriasis or psoriatic arthritis weighing more than 100 kg had lower median serum ustekinumab concentrations compared with those subjects weighing 100 kg or less. The median trough serum concentrations of ustekinumab in subjects of higher weight (greater than 100 kg) in the 90 mg group were comparable to those in subjects of lower weight (100 kg or less) in the 45 mg group.

Age: Geriatric Population
A population pharmacokinetic analysis (N=106/1937 subjects with plaque psoriasis greater than or equal to 65 years old) was performed to evaluate the effect of age on the pharmacokinetics of ustekinumab. There were no apparent changes in pharmacokinetic parameters (clearance and volume of distribution) in subjects older than 65 years old.

Age: Pediatric Population
Following multiple recommended doses of ustekinumab in pediatric subjects 6 years of age and older with plaque psoriasis, steady-state serum concentrations of ustekinumab were achieved by Week 28. At Week 28, the mean ±SD steady-state trough serum ustekinumab concentrations were 0.36 ± 0.26 mcg/mL and 0.54 ± 0.43 mcg/mL, respectively, in pediatric subjects 6 to 11 years of age and pediatric subjects 12years of age and older .
Overall, the observed steady-state ustekinumab trough concentrations in pediatric subjects with plaque psoriasis were within the range of those observed for adult subjects with plaque psoriasis and adult subjects with PsA after administration of ustekinumab.

Drug Interaction Studies
The effects of IL-12 or IL-23 on the regulation of CYP450 enzymes were evaluated in an in vitrostudy using human hepatocytes, which showed that IL-12 and/or IL-23 at levels of 10 ng/mL did not alter human CYP450 enzyme activities (CYP1A2, 2B6, 2C9, 2C19, 2D6, or 3A4).

No clinically significant changes in exposure of caffeine (CYP1A2 substrate), warfarin (CYP2C9 substrate), omeprazole (CYP2C19 substrate), dextromethorphan (CYP2D6 substrate), or midazolam (CYP3A substrate) were observed when used concomitantly with ustekinumab at the approved recommended dosage in subjects with Crohn’s disease [ see Drug Interactions (7.2)].

Population pharmacokinetic analyses indicated that the clearance of ustekinumab was not impacted by concomitant MTX, NSAIDs, and oral corticosteroids, or prior exposure to a TNF blocker in subjects with psoriatic arthritis.
In subjects with Crohn’s disease and ulcerative colitis, population pharmacokinetic analyses did not indicate changes in ustekinumab clearance with concomitant use of corticosteroids or immunomodulators (AZA, 6-MP, or MTX); and serum ustekinumab concentrations were not impacted by concomitant use of these medications.

13 NONCLINICAL TOXICOLOGY

13.1 Carcinogenesis, Mutagenesis, Impairment of Fertility

Animal studies have not been conducted to evaluate the carcinogenic or mutagenic potential of ustekinumab products. Published literature showed that administration of murine IL-12 caused an anti-tumor effect in mice that contained transplanted tumors and IL-12/IL-23p40 knockout mice or mice treated with anti-IL-12/IL-23p40 antibody had decreased host defense to tumors. Mice genetically manipulated to be deficient in both IL-12 and IL-23 or IL-12 alone developed UV-induced skin cancers earlier and more frequently compared to wild-type mice. The relevance of these experimental findings in mouse models for malignancy risk in humans is unknown.

No effects on fertility were observed in male cynomolgus monkeys that were administered ustekinumab at subcutaneous doses up to 45 mg/kg twice weekly (45 times the MRHD on a mg/kg basis) prior to and during the mating period. However, fertility and pregnancy outcomes were not evaluated in mated females.

No effects on fertility were observed in female mice that were administered an analogous IL-12/IL-23p40 antibody by subcutaneous administration at doses up to 50 mg/kg, twice weekly, prior to and during early pregnancy.

13.2 Animal Toxicology and/or Pharmacology

In a 26-week toxicology study, one out of 10 monkeys subcutaneously administered 45 mg/kg ustekinumab twice weekly for 26 weeks had a bacterial infection.

14 CLINICAL STUDIES

14.1 Adult Plaque Psoriasis

Two multicenter, randomized, double-blind, placebo-controlled trials (Ps STUDY 1 and Ps STUDY 2) enrolled a total of 1996 subjects 18 years of age and older with plaque psoriasis who had a minimum body surface area involvement of 10%, and Psoriasis Area and Severity Index (PASI) score ≥12, and who were candidates for phototherapy or systemic therapy. Subjects with guttate, erythrodermic, or pustular psoriasis were excluded from the trials.

Ps STUDY 1 enrolled 766 subjects and Ps STUDY 2 enrolled 1230 subjects. The trials had the same design through Week 28. In both trials, subjects were randomized in equal proportion to placebo, 45 mg or 90 mg of ustekinumab. Subjects randomized to ustekinumab received 45 mg or 90 mg doses, regardless of weight, at Weeks 0, 4, and 16. Subjects randomized to receive placebo at Weeks 0 and 4 crossed over to receive ustekinumab (either 45 mg or 90 mg) at Weeks 12 and 16.

In both trials, subjects in all treatment groups had a median baseline PASI score ranging from approximately 17 to 18. Baseline PGA score was marked or severe in 44% of subjects in Ps STUDY 1 and 40% of subjects in Ps STUDY 2. Approximately two-thirds of all subjects had received prior phototherapy, 69% had received either prior conventional systemic or biologic therapy for the treatment of psoriasis, with 56% receiving prior conventional systemic therapy and 43% receiving prior biologic therapy. A total of 28% of subjects had a history of psoriatic arthritis.

In both trials, the endpoints were the proportion of subjects who achieved at least a 75% reduction in PASI score (PASI 75) from baseline to Week 12 and treatment success (cleared or minimal) on the Physician’s Global Assessment (PGA). The PGA is a 6-category scale ranging from 0 (cleared) to 5 (severe) that indicates the physician’s overall assessment of psoriasis focusing on plaque thickness/induration, erythema, and scaling.

Clinica Response

The results of Ps STUDY 1 and Ps STUDY 2 are presented in Table 7 below.

Table 7: Clinical Outcomes at week 12 in Adults with Plaque Psoriasis in Ps STUDY 1 and Ps STUDY 2

Week 12 | Ps STUDY 1 Ustekinumab |  |  | Ps STUDY 2 Ustekinumab
Week 12 | Placebo | 45 mg | 90 mg | Placebo | 45 mg | 90 mg
Subjects randomized | 255 | 255 | 256 | 410 | 409 | 411
PASI 75 response | 8 (3%) | 171 (67%) | 170 (66%) | 15 (4%) | 273 (67%) | 311 (76%)
PG A of Cleared or Minimal | 10 (4%) | 151 (59%) | 156 (61%) | 18 (4%) | 277 (68%) | 300 (73%)

Examination of age, gender, and race subgroups did not identify differences in response to ustekinumab among these subgroups.

In subjects who weighed 100 kg or less, response rates were comparable with both the 45 mg and 90 mg doses; however, in subjects who weighed greater than 100 kg, higher response rates were seen with 90 mg dosing compared with 45 mg dosing (Table 8 below).

Table 8: Clinical Outcomes by Weight at week 12 in Adult Subjects with Plaque Psoriasis in Ps STUDY 1 and Ps STUDY 2

 | Ps STUDY 1 Ustekinumab |  |  | Ps STUDY 2 Ustekinumab
 | Placebo | 45 mg | 90 mg | Placebo | 45 mg | 90 mg
Subjects randomized | 255 | 255 | 256 | 410 | 409 | 411
PASI 75 response*
≤100 kg | 4% | 74% | 65% | 4% | 73% | 78%
 | 6/166 | 124/168 | 107/164 | 12/290 | 218/297 | 225/289
>100 kg | 2% | 54% | 68% | 3% | 49% | 71%
 | 2/89 | 47/87 | 63/92 | 3/120 | 55/112 | 86/121
PGA of Cleared or Minimal*
≤100 kg | 4% | 64% | 63% | 5% | 74% | 75%
 | 7/166 | 108/168 | 103/164 | 14/290 | 220/297 | 216/289
>100 kg | 3% | 49% | 58% | 3% | 51% | 69%
 | 3/89 | 43/87 | 53/92 | 4/120 | 57/112 | 84/121
*Subjects were dosed with trial medication at Weeks 0 and 4.

Subjects in Ps STUDY 1 who were PASI 75 responders at both Weeks 28 and 40 were re-randomized at Week 40 to either continued dosing of ustekinumab (ustekinumab at Week 40) or to withdrawal of therapy (placebo at Week 40). At Week 52, 89% (144/162) of subjects re-randomized to ustekinumab treatment were PASI 75 responders compared with 63% (100/159) of subjects re-randomized to placebo (treatment withdrawal after Week 28 dose). The median time to loss of PASI 75 response among the subjects randomized to treatment withdrawal was 16 weeks.

14.2 Pediatric Subjects with Plaque Psoriasis

A multicenter, randomized, double blind, placebo-controlled trial (Ps STUDY 3) enrolled 110 pediatric subjects 12 years of age and older with a minimum BSA involvement of 10%, a PASI score greater than or equal to 12, and a PGA score greater than or equal to 3, who were candidates for phototherapy or systemic therapy and whose disease was inadequately controlled by topical therapy.

Subjects were randomized to receive placebo (n = 37), the recommended dose of ustekinumab (n = 36), or one-half the recommended dose of ustekinumab (n = 37) by subcutaneous injection at Weeks 0 and 4 followed by dosing every 12 weeks (q12w). The recommended dose of ustekinumab was 0.75 mg/kg for subjects weighing less than 60 kg, 45 mg for subjects weighing 60 kg to 100 kg, and 90 mg for subjects weighing greater than 100 kg. At Week 12, subjects who received placebo were crossed over to receive ustekinumab at the recommended dose or one-half the recommended dose.

Of the pediatric subjects, approximately 63% had prior exposure to phototherapy or conventional systemic therapy and approximately 11% had prior exposure to biologics.

The endpoints were the proportion of subjects who achieved a PGA score of cleared (0) or minimal (1), PASI 75, and PASI 90 at Week 12. Subjects were followed for up to 60 weeks following first administration of trial agent.

Clinical Response

The efficacy results at Week 12 for Ps STUDY 3 are presented in Table 9.

Table 9: Efficacy Results at Week 12 in pediatric subjects 12 Years of Age and Older with Plaque Psoriasis in Ps STUDY 3

 | Ps STUDY 3
 | Placebo n (%) | Ustekinumab* n (%)
N | 37 | 36
PGA
PGA of cleared (0) or minimal (1) | 2 (5.4%) | 25 (69.4%)
PASI
PASI 75 responders | 4 (10.8%) | 29 (80.6%)
PASI 90 responders | 2 (5.4%) | 22 (61.1%)
* Using the weight-based dosage regimen specified in Table 1.

14.3 Psoriatic Arthritis

The safety and efficacy of ustekinumab was assessed in 927 subjects (PsA STUDY 1, n=615; PsA STUDY 2, n=312), in two randomized, double-blind, placebo-controlled trials in adult subjects 18 years of age and older with active PsA (≥5 swollen joints and ≥5 tender joints) despite nonsteroidal anti-inflammatory (NSAID) or disease modifying antirheumatic (DMARD) therapy. Subjects in these trials had a diagnosis of PsA for at least 6 months. Subjects with each subtype of PsA were enrolled, including polyarticular arthritis with the absence of rheumatoid nodules (39%), spondylitis with peripheral arthritis (28%), asymmetric peripheral arthritis (21%), distal interphalangeal involvement (12%) and arthritis mutilans (0.5%). Over 70% and 40% of the patients, respectively, had enthesitis and dactylitis at baseline.

Subjects were randomized to receive treatment with ustekinumab 45 mg, 90 mg, or placebo subcutaneously at Weeks 0 and 4 followed by every 12 weeks (q12w) dosing. Approximately 50% of subjects continued on stable doses of MTX (≤25 mg/week). The primary endpoint was the percentage of subjects achieving ACR 20 response at Week 24.

In PsA STUDY 1 and PsA STUDY 2, 80% and 86% of the subjects, respectively, had been previously treated with DMARDs. In PsA STUDY 1, previous treatment with anti-tumor necrosis factor (TNF)-α agent was not allowed. In PsA STUDY 2, 58% (n=180) of the subjects had been previously treated with TNF blocker, of whom over 70% had discontinued their TNF blocker treatment for lack of efficacy or intolerance at any time.

Clinical Response

In both trials, a greater proportion of subjects achieved ACR 20, ACR 50 and PASI 75 response in the ustekinumab 45 mg and 90 mg groups compared to placebo at Week 24 (see Table 10). ACR 70 responses were also higher in the ustekinumab 45 mg and 90 mg groups, although the difference was only numerical (p=NS) in STUDY 2. Responses were consistent in subjects treated with ustekinumab alone or in combination with methotrexate. Responses were similar in subjects regardless of prior TNFα exposure.

Table 10: ACR 20, ACR 50, ACR 70 and PASI 75 responses in PsA STUDY 1 and PsA STUDY 2 at Week 24

 | Ps STUDY 1 Ustekinumab |  |  | Ps STUDY 2 Ustekinumab
 | Placebo | 45 mg | 90 mg | Placebo | 45 mg | 90 mg
Number of patients randomized | 206 | 205 | 204 | 104 | 103 | 105
ACR 20 response, N (%) | 47 (23%) | 87 (42%) | 101 (50%) | 21 (20%) | 45 (44%) | 46 (44%)
ACR 50 response, N (%) | 18 (9%) | 51 (25%) | 57 (28%) | 7 (7%) | 18 (17%) | 24 (23%)
ACR 70 response, N (%) | 5 (2%) | 25 (12%) | 29 (14%) | 3 (3%) | 7 (7%) | 9 (9%)
Numberofpatientswith ≥ 3% BSAa | 146 | 145 | 149 | 80 | 80 | 81
PASI 75 response, N (%) | 16 (11%) | 83 (57%) | 93 (62%) | 4 (5%) | 41 (51%) | 45 (56%)
aNumber of patients with ≥ 3% BSA psoriasis skin involvement at baseline

The percent of patients achieving ACR 20 responses by visit is shown in Figure 1.

Figure 1: Percent of patients achieving ACR 20 response through Week 24

The results of the components of the ACR response criteria are shown in Table 11.

Table 11: Mean change from baseline in ACR components at Week 24

 | PsA STUDY 1 Ustekinumab
 | Placebo (N = 206) | 45 mg (N = 205) | 90 mg (N = 204)
Number of swollen jointsa
Baseline | 15 | 12 | 13
Mean Change at Week 24 | -3 | -5 | -6
Number of tender jointsb
Baseline | 25 | 22 | 23
Mean Change at Week 24 | -4 | -8 | -9
Patient’s assessment of painc
Baseline | 6.1 | 6.2 | 6.6
Mean Change at Week 24 | -0.5 | -2.0 | -2.6
Patient global assessmentc
Baseline | 6.1 | 6.3 | 6.4
Mean Change at Week 24 | -0.5 | -2.0 | -2.5
Physician global assessmentc
Baseline | 5.8 | 5.7 | 6.1
Mean Change at Week 24 | -1.4 | -2.6 | -3.1
Disability index (HAQ)d
Baseline | 1.2 | 1.2 | 1.2
Mean Change at Week 24 | -0.1 | -0.3 | -0.4
CRP (mg/dL)e
Baseline | 1.6 | 1.7 | 1.8
Mean Change at Week 24 | 0.01 | -0.5 | -0.8
aNumber of swollen joints counted (0-66)
bNumber of tender joints counted (0-68)
cVisual analogue scale; 0= best, 10=worst.
dDisability Index of the Health Assessment Questionnaire; 0 = best, 3 = worst, measures the patient’s ability to perform the following: dress/groom, arise, eat, walk, reach, grip, maintain hygiene, and maintain daily activity.
eCRP: (Normal Range 0.0-1.0 mg/dL)

An improvement in enthesitis and dactylitis scores was observed in each ustekinumab group compared with placebo at Week 24.

Physical Function
Ustekinumab-treated subjects showed improvement in physical function compared to subjects receiving placebo as assessed by HAQ-DI at Week 24. In both trials, the proportion of HAQ-DI responders (≥0.3 improvement in HAQ-DI score) was greater in the ustekinumab 45 mg and 90 mg groups compared to placebo at Week 24.

14.4 Crohn’s Disease

Ustekinumab was evaluated in three randomized, double-blind, placebo-controlled clinical trials in adult subjects with moderately to severely active Crohn’s disease (Crohn’s Disease Activity Index [CDAI] score of 220 to 450). There were two 8-week intravenous induction trials (CD-1 and CD-2) followed by a 44-week subcutaneous randomized withdrawal maintenance trial (CD-3) representing 52 weeks of therapy. Subjects in CD-1 had failed or were intolerant to treatment with one or more TNF blockers, while subjects in CD-2 had failed or were intolerant to treatment with immunomodulators or corticosteroids, but never failed treatment with a TNF blocker.

Trials CD-1 and CD-2
In trials CD-1 and CD-2, 1409 subjects were randomized, of whom 1368 (CD-1, n=741; CD-2, n=627) were included in the final efficacy analysis. Induction of clinical response (defined as a reduction in CDAI score of greater than or equal to 100 points or CDAI score of less than 150) at Week 6 and clinical remission (defined as a CDAI score of less than 150) at Week 8 were evaluated. In both trials, subjects were randomized to receive a single intravenous administration of ustekinumab at either approximately 6 mg/kg, placebo (see Table 3), or 130 mg (a lower dose than recommended).
In trial CD-1, subjects had failed or were intolerant to prior treatment with a TNF blocker: 29% subjects had an inadequate initial response (primary non- responders), 69% responded but subsequently lost response (secondary non-responders) and 36% were intolerant to a TNF blocker. Of these subjects, 48% failed or were intolerant to one TNF blocker and 52% had failed 2 or 3 prior TNF blockers. At baseline and throughout the trial, approximately 46% of the subjects were receiving corticosteroids and 31% of the subjects were receiving immunomodulators (AZA, 6-MP, MTX). The median baseline CDAI score was 319 in the ustekinumab approximately 6 mg/kg group and 313 in the placebo group.

In trial CD-2, subjects had failed or were intolerant to prior treatment with corticosteroids (81% of subjects), at least one immunomodulator (6-MP, AZA, MTX; 68% of subjects), or both (49% of subjects). Additionally, 69% never received a TNF blocker and 31% previously received but had not failed a TNF blocker. At baseline, and throughout the trial, approximately 39% of the subjects were receiving corticosteroids and 35% of the subjects were receiving immunomodulators (AZA, 6-MP, MTX). The median baseline CDAI score was 286 in the ustekinumab and 290 in the placebo group.

In these induction trials, a greater proportion of subjects treated with ustekinumab (at the recommended dose of approximately 6 mg/kg dose) achieved clinical response at Week 6 and clinical remission at Week 8 compared to placebo (see Table 12 for clinical response and remission rates). Clinical response and remission were significant as early as Week 3 in ustekinumab -treated subjects and continued to improve through Week 8.

Table 12: Induction of Clinical Response and Remission in CD-1* and CD-2**

 | CD-1 n = 741 |  |  | CD-2 n = 627
 | Placebo N = 247 | Ustekinumab† N = 249 | Treatment Difference and 95% CI | Placebo N = 209 | Ustekinumab† N = 209 | Treatment difference and 95% CI
Clinical Response (100 point), Week 6 | 53 (21%) | 84 (34%)a | 12% (4%, 20%) | 60 (29%) | 116 (56%)b | 27% (18%, 36%)
Clinical Remission, Week 8 | 18 (7%) | 52 (21%)b | 14% (8%, 20%) | 41 (20%) | 84 (40%)b | 26% (17%, 35%)
Clinical Response (100 point), Week 8 | 50 (20%) | 94 (38%)b | 18% (10%, 25%) | 67 (32%) | 121 (58%)b | 21% (12%, 29%)
70 Point Response, Week 6 | 75 (30%) | 109 (44%)a | 13% (5%, 22%) | 81 (39%) | 135 (65%)b | 26% (17%, 35%)
70 Point Response, Week 3 | 67 (27%) | 101 (41%)a | 13% (5%, 22%) | 66 (32%) | 106 (51%)b | 19% (10%, 28%)
Clinical remission is defined as CDAI score < 150; Clinical response is defined as reduction in CDAI score by at least 100 points or being in clinical remission: 70 point response is defined as reduction in CDAI score by at least 70 points
* Patient population consisted of patients who failed or were intolerant to TNF blocker therapy
** Patient population consisted of patients who failed or were intolerant to corticosteroids or immunomodulators (e.g., 6-MP, AZA, MTX) and previously received but not failed a TNF blocker or were never treated with a TNF blocker.
† Infusion dose of ustekinumab using the weight-based dosage regimen specified in Table 3.
a0.001≤ p < 0.01
bp < 0.001

Trial CD-3
The maintenance trial (CD-3), evaluated 388 subjects who achieved clinical response (≥100 point reduction in CDAI score) at Week 8 with either induction dose of ustekinumab in trials CD-1 or CD-2. Subjects were randomized to receive a subcutaneous maintenance regimen of either 90 mg ustekinumab every 8 weeks or placebo for 44 weeks (see Table 13).

Table 13: Clinical Response and Remission in CD-3 (Week 44; 52 weeks from initiation of the induction dose)

 | Placebo* N = 131† | 90 mg Ustekinumab every 8 weeks N = 128† | Treatmentdifference and 95% CI
Clinical Remission | 47 (36%) | 68 (53%)a | 17% (5%, 29%)
Clinical Response | 58 (44%) | 76 (59%)b | 15% (3%, 27%)
Clinical Remission in patients in remission at the start of maintenance therapy** | 36/79 (46%) | 52/78 (67%)a | 21% (6%, 36%)
Clinical remission is defined as CDAI score < 150; Clinical response is defined as reduction in CDAI of at least 100 points or being in clinical remission
*The placebo group consisted of patients who were in response to ustekinumab and were randomized to receive placebo at the start of maintenance therapy.
** Patients in remission at the end of maintenance therapy who were in remission at the start of maintenance therapy. This does not account for any other time point during maintenance therapy.
†Patients who achieved clinical response to ustekinumab at the end of the induction study.
ap < 0.01
b0.01≤ p < 0.05

At Week 44, 47% of subjects who received ustekinumab were corticosteroid-free and in clinical remission, compared to 30% of subjects in the placebo group.

At Week 0 of trial CD-3, 34/56 (61%) ustekinumab-treated subjects who previously failed or were intolerant to TNF blocker therapies were in clinical remission and 23/56 (41%) of these subjects were in clinical remission at Week 44. In the placebo arm, 27/61 (44%) subjects were in clinical remission at Week 0 while 16/61 (26%) of these subjects were in remission at Week 44.

At Week 0 of trial CD-3, 46/72 (64%) ustekinumab-treated subjects who had previously failed immunomodulator therapy or corticosteroids (but not TNF blockers) were in clinical remission and 45/72 (63%) of these subjects were in clinical remission at Week 44. In the placebo arm, 50/70 (71%) of these subjects were in clinical remission at Week 0 while 31/70 (44%) were in remission at Week 44. In the subset of these subjects who were also naïve to TNF blockers, 34/52 (65%) of ustekinumab-treated subjects were in clinical remission at Week 44 as compared to 25/51 (49%) in the placebo arm.

Subjects who were not in clinical response 8 weeks after ustekinumab induction were not included in the primary efficacy analyses for trial CD-3; however, these subjects were eligible to receive a 90 mg subcutaneous injection of ustekinumab upon entry into trial CD-3. Of these subjects, 102/219 (47%) achieved clinical response eight weeks later and were followed for the duration of the trial.

14.5 Ulcerative Colitis

Ustekinumab was evaluated in two randomized, double-blind, placebo-controlled clinical trials [UC-1 and UC-2 (NCT02407236)] in adult subjects with moderately to severely active ulcerative colitis who had an inadequate response to or failed to tolerate a biologic (i.e., TNF blocker and/or vedolizumab), corticosteroids, and/or 6-MP or AZA therapy. The 8-week intravenous induction trial (UC-1) was followed by the 44-week subcutaneous randomized withdrawal maintenance trial (UC-2) for a total of 52 weeks of therapy.

Disease assessment was based on the Mayo score, which ranged from 0 to 12 and has four subscores that were each scored from 0 (normal) to 3 (most severe): stool frequency, rectal bleeding, findings on centrally-reviewed endoscopy, and physician global assessment. Moderately to severely active ulcerative colitis was defined at baseline (Week 0) as Mayo score of 6 to 12, including a Mayo endoscopy subscore ≥2. An endoscopy score of 2 was defined by marked erythema, absent vascular pattern, friability, erosions; and a score of 3 was defined by spontaneous bleeding, ulceration. At baseline, subjects had a median Mayo score of 9, with 84% of subjects having moderate disease (Mayo score 6-10) and 15% having severe disease (Mayo score 11-12).

Subjects in these trials may have received other concomitant therapies including aminosalicylates, immunomodulatory agents (AZA, 6-MP, or MTX), and oral corticosteroids (prednisone).

Trial UC-1
In UC-1, 961 subjects were randomized at Week 0 to a single intravenous administration of ustekinumab of approximately 6 mg/kg, 130 mg (a lower dose than recommended), or placebo. Subjects enrolled in UC-1 had to have failed therapy with corticosteroids, immunomodulators or at least one biologic. A total of 51% had failed at least one biologic and 17% had failed both a TNF blocker and an integrin receptor blocker. Of the total population, 46% had failed corticosteroids or immunomodulators but were biologic-naïve and an additional 3% had previously received but had not failed a biologic. At induction baseline and throughout the trial, approximately 52% subjects were receiving oral corticosteroids, 28% subjects were receiving immunomodulators (AZA, 6-MP, or MTX) and 69% subjects were receiving aminosalicylates.

The primary endpoint was clinical remission at Week 8. Clinical remission with a definition of: Mayo stool frequency subscore of 0 or 1, Mayo rectal bleeding subscore of 0 (no rectal bleeding), and Mayo endoscopy subscore of 0 or 1 (Mayo endoscopy subscore of 0 defined as normal or inactive disease and Mayo subscore of 1 defined as presence of erythema, decreased vascular pattern and no friability) is provided in Table 14.

The secondary endpoints were clinical response, endoscopic improvement, and histologic-endoscopic mucosal improvement. Clinical response with a definition of (≥ 2 points and ≥ 30% decrease in modified Mayo score, defined as 3-component Mayo score without the Physician’s Global Assessment, with either a decrease from baseline in the rectal bleeding subscore ≥1 or a rectal bleeding subscore of 0 or 1), endoscopic improvement with a definition of Mayo endoscopy subscore of 0 or 1, and histologic-endoscopic mucosal improvement with a definition of combined endoscopic improvement and histologic improvement of the colon tissue [neutrophil infiltration in <5% of crypts, no crypt destruction, and no erosions, ulcerations, or granulation tissue] are provided in Table 14.

In UC-1, a significantly greater proportion of subjects treated with ustekinumab (at the recommended dose of approximately 6 mg/kg dose) were in clinical remission and response and achieved endoscopic improvement and histologic-endoscopic mucosal improvement compared to placebo (see Table 14).

Table 14: Proportion of Subjects Meeting Efficacy Endpoints at Week 8 in UC-1

Endpoint | Placebo N = 319 |  | Ustekinumab† N = 322 |  | Treatmentdifferenceand 97.5% CIa
Endpoint | N | % | N | % | Treatmentdifferenceand 97.5% CIa
Clinical Remission* | 22 | 7% | 62 | 19% | 12% (7%, 18%)b
Bio-naïve⸸ | 14/151 | 9% | 36/147 | 24%
Prior biologic failure | 7/161 | 4% | 24/166 | 14%
Endoscopic Improvement§ | 40 | 13% | 80 | 25% | 12% (6%, 19%)b
Bio-naïve⸸ | 28/151 | 19% | 43/147 | 29%
Prior biologic failure | 11/161 | 7% | 34/166 | 20%
Clinical Response† | 99 | 31% | 186 | 58% | 27% (18%, 35%)b
Bio-naïve⸸ | 55/151 | 36% | 94/147 | 64%
Prior biologic failure | 42/161 | 26% | 86/166 | 52%
Histologic-Endoscopic Mucosal Improvement‡ | 26 | 8% | 54 | 17% | 9% (3%, 14%)b
Bio-naïve⸸ | 19/151 | 13% | 30/147 | 20%
Prior biologic failure | 6/161 | 4% | 21/166 | 13%
†Infusion dose of ustekinumab using the weight-based dosage regimen specified in Table 3.
⸸An additional 7 patients on placebo and 9 patients on ustekinumab (6 mg/kg) had been exposed to, but had not failed, biologics.
* Clinical remission was defined as Mayo stool frequency subscore of 0 or 1, Mayo rectal bleeding subscore of 0, and Mayo endoscopy subscore of 0 or 1 (modified so that 1 does not include friability).
§Endoscopic improvement was defined as Mayo endoscopy subscore of 0 or 1 (modified so that 1 does not include friability).
†Clinical response was defined as a decrease from baseline in the modified Mayo score by ≥30% and ≥2 points, with either a decrease from baseline in the rectal bleeding subscore ≥1 or a rectal bleeding subscore of 0 or 1.
‡Histologic-endoscopic mucosal improvement was defined as combined endoscopic improvement (Mayo endoscopy subscore of 0 or 1) and histologic improvement of the colon tissue (neutrophil infiltration in <5% of crypts, no crypt destruction, and no erosions, ulcerations, or granulation tissue).
aAdjusted treatment difference (97.5% CI)
bp < 0.001

The relationship of histologic-endoscopic mucosal improvement, as defined in UC-1, at Week 8 to disease progression and long-term outcomes was not evaluated during UC-1.

Rectal Bleeding and Stool Frequency Subscores
Decreases in rectal bleeding and stool frequency subscores were observed as early as Week 2 in ustekinumab-treated subjects.

Trial UC-2
The maintenance trial (UC-2) evaluated 523 subjects who achieved clinical response 8 weeks following the intravenous administration of either induction dose of ustekinumab in UC-1. These subjects were randomized to receive a subcutaneous maintenance regimen of either 90 mg ustekinumab every 8 weeks, or every 12 weeks (a lower dose than recommended), or placebo for 44 weeks.

The primary endpoint was the proportion of subjects in clinical remission at Week 44. The secondary endpoints included the proportion of subjects maintaining clinical response at Week 44, the proportion of subjects with endoscopic improvement at Week 44, the proportion of subjects with corticosteroid-free clinical remission at Week 44, and the proportion of subjects maintaining clinical remission at Week 44 among subjects who achieved clinical remission 8 weeks after induction.

Results of the primary and secondary endpoints at Week 44 in subjects treated with ustekinumab at the recommended dosage (90 mg every 8 weeks) compared to the placebo are shown in Table 15.

Table 15: Efficacy Endpoints of Maintenance at Week 44 in UC-2 (52 Weeks from Initiation of the Induction Dose)

End point | Placebo* N = 175† |  | 90 mg Ustekinumab every 8 weeks N = 176 |  | Treatmentdifferenceand 95% CI
End point | N | % | N | % | Treatmentdifferenceand 95% CI
Clinical Remission** | 46 | 26% | 79 | 45% | 19% (9%, 28%)a
Bio-naïve⸸ | 30/84 | 36% | 39/79 | 49%
Prior biologic failure | 16/88 | 18% | 37/91 | 41%
Maintenance of Clinical Response at Week 44† | 84 | 48% | 130 | 74% | 26%
Maintenance of Clinical Response at Week 44† |  |  |  |  | (16%, 36%)a
Bio-naïve⸸ | 49/84 | 58% | 62/79 | 78%
Prior biologic failure | 35/88 | 40% | 64/91 | 70%
Endoscopic Improvement§ | 47 | 27% | 83 | 47% | 20% (11%, 30%)a
Bio-naïve⸸ | 29/84 | 35% | 42/79 | 53%
Prior biologic failure | 18/88 | 20% | 38/91 | 42%
Corticosteroid-free Clinical Remission‡ | 45 | 26% | 76 | 43% | 17% (8%, 27%)a
Bio-naïve⸸ | 30/84 | 36% | 38/79 | 48%
Prior biologic failure | 15/88 | 17% | 35/91 | 38%
Maintenance of Clinical Remission at Week 44 in patients who achieved clinical remission 8 weeks after induction | 18/50 | 36% | 27/41 | 66% | 31% (12%, 50%)b
Bio-naïve⸸ | 12/27 | 44% | 14/20 | 70%
Prior biologic failure | 6/23 | 26% | 12/18 | 67%
⸸ An additional 3 patients on placebo and 6 patients on ustekinumab had been exposed to, but had not failed, biologics.
* The placebo group consisted of patients who were in response to ustekinumab and were randomized to receive placebo at the start of maintenance therapy.
** Clinical remission was defined as Mayo stool frequency subscore of 0 or 1, Mayo rectal bleeding subscore of 0, and Mayo endoscopy subscore of 0 or 1 (modified so that 1 does not include friability).
† Clinical response was defined as a decrease from baseline in the modified Mayo score by ≥30% and ≥2 points, with either a decrease from baseline in the rectal bleeding subscore ≥1 or a rectal bleeding subscore of 0 or 1.
§ Endoscopic improvement was defined as Mayo endoscopy subscore of 0 or 1 (modified so that 1 does not include friability).
‡ Corticosteroid-free clinical remission was defined as patients in clinical remission and not receiving corticosteroids at Week 44.
a p =<0.001
b p=0.004

Other Endpoints
Week 16 Responders to Ustekinumab Induction
Subjects who were not in clinical response 8 weeks after induction with ustekinumab in UC-1 were not included in the primary efficacy analyses for trial UC-2; however, these subjects were eligible to receive a 90 mg subcutaneous injection of ustekinumab at Week 8. Of these subjects, 55/101 (54%) achieved clinical response eight weeks later (Week 16) and received ustekinumab 90 mg subcutaneously every 8 weeks during the UC-2 trial. At Week 44, there were 97/157 (62%) subjects who maintained clinical response and there were 51/157 (32%) who achieved clinical remission.

Histologic-Endoscopic Mucosal Improvement at Week 44
The proportion of subjects achieving histologic-endoscopic mucosal improvement during maintenance treatment in UC-2 was 75/172 (44%) among subjects on ustekinumab and 40/172 (23%) in subjects on placebo at Week 44. The relationship of histologic-endoscopic mucosal improvement, as defined in UC-2, at Week 44 to progression of disease or long-term outcomes was not evaluated in UC-2.

Endoscopic Normalization
Normalization of endoscopic appearance of the mucosa was defined as a Mayo endoscopic subscore of 0. At Week 8 in UC-1, endoscopic normalization was achieved in 25/322 (8%) of subjects treated with ustekinumab and 12/319 (4%) of subjects in the placebo group. At Week 44 of UC-2, endoscopic normalization was achieved in 51/176 (29%) of subjects treated with ustekinumab and in 32/175 (18%) of subjects in placebo group.

15 REFERENCES

^1 Surveillance, Epidemiology, and End Results (SEER) Program (www.seer.cancer.gov) SEER*Stat Database: Incidence - SEER 6.6.2 Regs Research Data, Nov 2009 Sub (1973-2007) - Linked To County Attributes - Total U.S., 1969-2007 Counties, National Cancer Institute, DCCPS, Surveillance Research Program, Surveillance Systems Branch, released April 2010, based on the November 2009 submission.

16 HOW SUPPLIED/STORAGE AND HANDLING

IMULDOSA (ustekinumab-srlf) injection is a sterile, preservative-free, clear to slightly opalescent and colorless to slightly yellow solution. It is supplied as individually packaged, single-dose prefilled syringes or single-dose vials.

For Subcutaneous Use

Prefilled Syringes

- 45 mg/0.5 mL (NDC 51407-929-11)
- 90 mg/mL (NDC 51407-930-11)

Each prefilled syringe is equipped with a 29-gauge fixed ½ inch needle, a needle safety guard, and a needle cover that does not contain latex.

For Intravenous Infusion

Single-dose Vial

- 130 mg/26 mL (5 mg/mL) (NDC 51407-931-11)

Storage and Stability

Store IMULDOSA vials and prefilled syringes refrigerated between 2ºC to 8ºC (36ºF to 46ºF).
Store IMULDOSA vials upright.
Keep the product in the original carton to protect from light until the time of use. Do not freeze. Do not shake.

If needed, individual prefilled syringes may be stored at room temperature up to 30°C (86°F) for a maximum single period of up to 30 days in the original carton to protect from light. Record the date when the prefilled syringe is first removed from the refrigerator on the carton in the space provided. Once a syringe has been stored at room temperature, do not return to the refrigerator. Discard the syringe if not used within 30 days at room temperature storage. Do not use IMULDOSA after the expiration date on the carton or on the prefilled syringe.

17 PATIENT COUNSELING INFORMATION

Advise the patient and/or caregiver to read the FDA-approved patient labeling (Medication Guide and Instructions for Use).

Infections

Inform patients that IMULDOSA may lower the ability of their immune system to fight infections and to contact their healthcare provider immediately if they develop any signs or symptoms of infection [see Warnings and Precautions (5.1)].

Malignancies

Inform patients of the risk of developing malignancies while receiving IMULDOSA [see Warnings and Precautions (5.4)].

Serious Hypersensitivityand Reactions

- Inform patients that serious hypersensitivity reactions have been reported with intravenous and subcutaneous administration of ustekinumab products. Instruct patients to discontinue IMULDOSA and seek immediate medical attention if they experience any signs or symptoms of hypersensitivity reactions [see Warnings and Precautions (5.5)].

Posterior Reversible Encephalopathy Syndrome (PRES)

Inform patients to immediately contact their healthcare provider if they experience signs and symptoms of PRES (which may include headache, seizures, confusion, or visual disturbances) [see Warnings and Precautions (5.6)].

Immunizations

Inform patients that IMULDOSA can interfere with the usual response to immunizations and that they should avoid live vaccines [see Warnings and Precautions (5.7)].

Administration

Instruct patients to follow sharps disposal recommendations, as described in the Instructions for Use.

Manufactured by:
Accord BioPharma Inc.
8041 Arco Corporate Drive, Suite 200
Raleigh, North Carolina (NC), 27617 USA
US License No. 2105

Marketed by:
GSMS, Inc.
Camarillo, CA 93012 USA

MEDICATION GUIDE
IMULDOSA (im ul doe' sah)
(ustekinumab-srlf)
injection, for subcutaneous or intravenous use

What is the most important information I should know about IMULDOSA?
IMULDOSA is a medicine that affects your immune system. IMULDOSA can increase your risk of having serious side effects, including:

- Serious infections.IMULDOSA may lower the ability of your immune system to fight infections and may increase your risk of infections. Some people have serious infections during treatment with ustekinumab products, including tuberculosis (TB), and infections caused by bacteria, fungi, or viruses. Some people have to be hospitalized for treatment of their infection.
  - Your healthcare provider should check you for TB before starting IMULDOSA.
  - If your healthcare provider feels that you are at risk for TB, you may be treated with medicine for TB before you begin treatment with IMULDOSA and during treatment with IMULDOSA.
  - Your healthcare provider should watch you closely for signs and symptoms of TB while you are being treated with IMULDOSA.

You should not start IMULDOSA if you have any kind of infection unless your healthcare provider says it is okay.

Before starting IMULDOSA, tell your doctor if you:

- think you have an infection or have symptoms of an infection such as:

- fever, sweat, or chills
- muscle aches
- cough
- shortness of breath
- blood in phlegm

- weight loss
- warm, red, or painful skin or sores on your body
- diarrhea or stomach pain
- burning when you urinate or urinate more often than normal
- feel very tired

- are being treated for an infection or have any open cuts.
- get a lot of infections or have infections that keep coming back.
- have TB, or have been in close contact with someone with TB.
  After starting IMULDOSA, call your doctor right away if you have any symptoms of an infection (see above). These may be signs of infections such as chest infections, or skin infections or shingles that could have serious complications. IMULDOSA can make you more likely to get infections or make an infection that you have worse.

- People who havea genetic problem where the body does not make any of the proteins interleukin 12 (IL-12) and interleukin 23 (IL-23) are at a higher risk for certain serious infections. These infections can spread throughout the body and cause death. People who take IMULDOSA may also be more likely to get these infections.
- Cancers. IMULDOSA may decrease the activity of your immune system and increase your risk for certain types of cancers. Tell your doctor if you have ever had any type of cancer. Some people who are receiving ustekinumab products and have risk factors for skin cancer have developed certain types of skin cancers. During your treatment with IMULDOSA, tell your doctor if you develop any new skin growths.

What is IMULDOSA?
IMULDOSA is a prescription medicine used to treat:

- adults and children 6 years and older with moderate to severe psoriasis who may benefit from taking injections or pills (systemic therapy) or phototherapy (treatment using ultraviolet light alone or with pills).
- adults and children 6 years and older with active psoriatic arthritis.
- adults 18 years and older with moderately to severely active Crohn’s disease.
- adults 18 years and older with moderately to severely active ulcerative colitis.

It is not known if IMULDOSA is safe and effective in children with Crohn’s disease or ulcerative colitis or in children less than 6 years of age with plaque psoriasis or psoriatic arthritis.

Who should not use IMULDOSA?

Do not use IMULDOSA if you are allergic to ustekinumab products or any of the ingredients in IMULDOSA. See the end of this Medication Guide for a complete list of ingredients in IMULDOSA.

Before you use or receive IMULDOSA, tell your doctor about all of your medical conditions, including if you:

- have any of the conditions or symptoms listed in the section “ What is the most important information I should know about IMULDOSA?”
- ever had an allergic reaction to ustekinumab products. Ask your healthcare provider if you are not sure.
- have recently received or are scheduled to receive an immunization (vaccine). People who are being treated with IMULDOSA should avoid receiving live vaccines. Tell your healthcare provider if anyone in your house needs a live vaccine. The viruses used in some types of live vaccines can spread to people with a weakened immune system and can cause serious problems. You should avoid receiving the BCG vaccine during the one year before receiving IMULDOSA or one year after you stop receiving IMULDOSA.
- have any new or changing lesions within psoriasis areas or on normal skin.
- are receiving or have received allergy shots, especially for serious allergic reactions. Allergy shots may not work as well for you during treatment with IMULDOSA. IMULDOSA may also increase your risk of having an allergic reaction to an allergy shot.
- receive or have received phototherapy for your psoriasis.
- are pregnant or plan to become pregnant. It is not known if IMULDOSA can harm your unborn baby. You and your healthcare provider should decide if you will receive IMULDOSA.
- are breastfeeding or plan to breastfeed. IMULDOSA can pass into your breast milk.
- Talk to your healthcare provider about the best way to feed your baby if you receive IMULDOSA.

Tell your healthcare provider about all the medicines you take, including prescription and over-the-counter medicines, vitamins, and herbal supplements.
Know the medicines you take. Keep a list of them to show your healthcare provider and pharmacist when you get a new medicine.

How should I use IMULDOSA?

- Use IMULDOSA exactly as the healthcare provider tells you to. The healthcare provider will determine the right dose of IMULDOSA, the amount for each injection, and how often it should be given. Be sure to keep all scheduled follow-up appointments.
- Adults with Crohn’s disease and ulcerative colitis will receive the first dose of IMULDOSA through a vein in the arm (intravenous infusion) in a healthcare facility by a healthcare provider. It takes at least 1 hour to receive the full dose of medicine. IMULDOSA will then be received as an injection under the skin (subcutaneous injection) 8 weeks after the first dose of IMULDOSA, as described below.
- Adults and children 6 years of age and older with plaque psoriasis or psoriatic arthritis will receive IMULDOSA as an injection under the skin as described below.
- Injecting IMULDOSA under the skin
  - IMULDOSA is intended for use under the guidance and supervision of a healthcare provider.
  - In children, it is recommended that IMULDOSA be administered by a healthcare provider. If a healthcare provider decides that you or a caregiver may give the injections of IMULDOSA at home, you or a caregiver should receive training on the right way to prepare and give the injections.
  - Do not try to inject IMULDOSA until you have been shown how to give the injections by a healthcare provider.
  - IMULDOSA can be injected under the skin in the upper arms, buttocks, upper legs (thighs) or stomach area (abdomen).
  - Do not give an injection in an area of the skin that is tender, bruised, red or hard.
  - Use a different injection site each time you use IMULDOSA.
- If you inject too much IMULDOSA, call the healthcare provider or Poison Help line at 1-800-222-1222, or go to the nearest emergency room right away.

Read the detailed Instructions for Use at the end of this Medication Guide for instructions about how to prepare and inject a dose of IMULDOSA, and how to properly throw away (dispose of) used needles and syringes. The syringe, needle and vial must never be re-used. After the rubber stopper is punctured, IMULDOSA can become contaminated by harmful bacteria which could cause an infection if re-used. Therefore, throw away any unused portion of IMULDOSA.

What should I avoid while using IMULDOSA?
You should not receive a live vaccine while taking IMULDOSA. See “Before you receive IMULDOSA, tell your healthcare provider about all of your medical conditions, including if you:”

What are the possible side effects of IMULDOSA?
IMULDOSA may cause serious side effects, including:

- See “ What is the most important information I should know about IMULDOSA?”
- Serious allergic reactions. Serious allergic reactions can occur with IMULDOSA. Stop using IMULDOSA and get medical help right away if you have any of the following symptoms of a serious allergic reaction:

- feeling faint
- swelling of your face, eyelids, tongue, or throat
- Trouble breathing

- chest discomfort
- skin rash

- Posterior Reversible Encephalopathy Syndrome (PRES).PRES is a rare condition that affects the brain and can cause death. Tell your healthcare provider right away if you get any symptoms of PRES during treatment with IMULDOSA, including:

- headache
- seizures

- confusion
- vision problems

- Lung inflammation. Cases of lung inflammation have happened in some people who receive ustekinumab products, and may be serious.
  These lung problems may need to be treated in a hospital. Tell your doctor right away if you develop shortness of breath or a cough that doesn’t go away during treatment with IMULDOSA.

The most common side effects of IMULDOSA include:

- nasal congestion, sore throat, and runny nose
- upper respiratory infections
- fever
- headache
- tiredness
- itching
- nausea and vomiting
- Influenza

- redness at the injection site
- vaginal yeast infections
- urinary tract infections
- sinus infection
- bronchitis
- diarrhea
- stomach pain
- joint pain

These are not all of the possible side effects of IMULDOSA. Call your doctor for medical advice about side effects. You may report side effects to FDA at 1-800-FDA-1088.
You may also report side effects to Accord BioPharma, Inc. at 1-866-941-7875.

How should I store IMULDOSA?

- Store IMULDOSA vials and prefilled syringes in a refrigerator between 36°F to 46°F (2°C to 8°C).
- Store IMULDOSA vials standing up straight.
- Store IMULDOSA in the original carton to protect it from light until time to use it.
- Do not freeze IMULDOSA.
- Do not shake IMULDOSA.
- If needed, individual IMULDOSA prefilled syringes may also be stored at room temperature up to 86ºF (30°C) for a maximum single period of up to 30 days in the original carton to protect from light.
- Record the date when the prefilled syringe is first removed from the refrigerator on the carton in the space provided.
- After a prefilled syringe has been stored at room temperature, do not return it to the refrigerator.
- Throw away (discard) the prefilled syringe if it is not used within 30 days at room temperature storage.
- Do not use IMULDOSA after the expiration date on the carton or on the prefilled syringe.

Keep IMULDOSA and all medicines out of the reach of children.

General information about the safe and effective use of IMULDOSA.
Medicines are sometimes prescribed for purposes other than those listed in a Medication Guide. Do not use IMULDOSA for a condition for which it was not prescribed. Do not give IMULDOSA to other people, even if they have the same symptoms that you have. It may harm them. You can ask your doctor or pharmacist for information about IMULDOSA that was written for health professionals.

What are the ingredients in IMULDOSA?
Active ingredient: ustekinumab-srlf
Inactive ingredients: Single-dose prefilled syringe for subcutaneous use contains histidine, L-histidine hydrochloride monohydrate, polysorbate 80, and sucrose. Single-dose vial for intravenous infusion contains edetate disodium, histidine, L-histidine hydrochloride monohydrate, methionine, polysorbate 80, and sucrose.
Manufactured by: Accord BioPharma Inc. 8041 Arco Corporate Drive, Suite 200, Raleigh, North Carolina (NC), 27617 USA.
US License No. 2105

Marketed by:
GSMS, Inc.
Camarillo, CA 93012 USA
For more information go to www.imuldosa.com or call 1-866-941-7875.

This Medication Guide has been approved by the U.S. Food and Drug Administration

Revised: 11/2025

INSTRUCTIONS FOR USE
IMULDOSA (im ul doe' sah)
(ustekinumab-srlf)
injection, for subcutaneous use

This Instructions for Use contains information on how to inject IMULDOSA using a prefilled syringe.

Read this Instructions for Use before you start using IMULDOSA. A healthcare provider should show you how to prepare and give the injection of IMULDOSA the right way.

If you cannot give the injection:

- ask your healthcare provider to help you, or
- ask someone who has been trained by a healthcare provider to give your injections.

Do not try to inject IMULDOSA until you have been shown how to inject IMULDOSA by a healthcare provider.

Important information You Need to Know Before Injecting IMULDOSA:

- For subcutaneous use only(inject directly under the skin).
- Before you start, check the carton to make sure that it is the right dose. You will have either 45 mg or 90 mg as prescribed by the healthcare provider.
  - If the dose is 45 mg, you will receive one 45 mg prefilled syringe.
  - If the dose is 90 mg, you will receive either one 90 mg prefilled syringe or two 45 mg prefilled syringes.
    If you receive two 45 mg prefilled syringes for a 90 mg dose, you will need to give two injections, one right after the other.
- Check the expiration date on the prefilled syringe and carton. If the expiration date has passed or if the prefilled syringe has been kept at room temperature up to 86°F (30°C) for longer than a maximum single period of 30 days or if the prefilled syringe has been stored above 86°F (30°C), do not use it. If the expiration date has passed or if the prefilled syringe has been stored above 86°F (30°C) or at room temperature for longer than 30 days, call the healthcare provider or pharmacist, or call 1-866-941-7875 for help.
- Make sure the syringe is not damaged.
- Check the prefilled syringe for any particles or discoloration. The liquid in the prefilled syringe should look clear to slightly opalescent and colorless to slightly yellow solution.
- Do not use if it is frozen, discolored, cloudy or has particles. Get a new prefilled syringe.
- Do not shake the prefilled syringe at any time.Shaking the prefilled syringe may damage the IMULDOSA medicine. If the prefilled syringe has been shaken, do not use it. Get a new prefilled syringe.
- To reduce the risk of accidental needle sticks, each prefilled syringe has a needle guard that is automatically activated to cover the needle after you have given the injection. Do not pull back on the plunger at any time.

Storing IMULDOSA prefilled syringes

- Store IMULDOSA prefilled syringes in the refrigerator between 36ºF to 46ºF (2ºC to 8ºC).
- Store IMULDOSA prefilled syringes in the original carton to protect from light .
- Do not freeze IMULODSA prefilled syringes.
- If needed, IMULDOSA prefilled syringe may be stored at room temperature up to 86°F (30°C) for a maximum single period of up to 30 days in the original carton to protect from light.
- Record the date when the prefilled syringe is removed from the refrigerator on the carton in the space provided.
- After a prefilled syringe has been stored at room temperature, do not return it to the refrigerator.
- Throw away (discard) the prefilled syringe if it is not used within 30 days at room temperature storage.

Keep IMULDOSA and all medicines out of the reach of children.

Gather the supplies you will need to prepare and to give the injection. (See Figure A)
You will need:

- antiseptic wipes
- cotton balls or gauze pads
- adhesive bandage
- your prescribed dose of IMULDOSA (See Figure B)
- FDA-cleared sharps disposal container. See “Step 4: Disposing of the syringes.”

Figure A

Figure B

To prevent early activation of the needle safety guard, do not touch the needle guard activation clips at any time during use.

Step 1: Preparing the injection.

- Choose a well-lit, clean, flat work surface.
- Wash your hands well with soap and warm water.
- Hold the prefilled syringe with the covered needle pointing upward.

Step 2: Preparing the injection site

- Choose an injection site around the stomach area (abdomen), buttocks, upper legs (thighs). If a caregiver is giving the injection, the outer area of the upper arms may also be used. (See Figure C)
- Use a different injection site for each injection. Do not give an injection in an area of the skin that is tender, bruised, red or hard.
- Clean the skin with an antiseptic wipe where you plan to give the injection.
- Do not touch this area again before giving the injection. Let the skin dry before injecting.
- Do not fan or blow on the clean area.

Figure C

*Areas in gray are recommended injection sites.

Step 3: Injecting IMULDOSA

- Remove the needle cover when you are ready to inject IMULDOSA.
- Do not the plunger or the plunger head while removing the needle cover.
- Hold the body of the prefilled syringe with one hand and pull the needle cover straight off. (See Figure D)
- Put the needle cover in the trash.
- You may also see a drop of liquid at the end of the needle. This is normal.
- Do not touch the needle or let it touch anything.
- Do not use the prefilled syringe if it is dropped without the needle cover in place.

Figure D

- Hold the body of the prefilled syringe in one hand between the thumb and index fingers. (See Figure E)

Figure E

- Do not pull back on the plunger at any time.
- Use the other hand to gently pinch the cleaned area of skin. Hold firmly.
- Use a quick, dart-like motion to insert the needle into the pinched skin at about a 45-degree angle. (See Figure F)

Figure F

- Inject all of the liquid by using your thumb to push in the plunger until the plunger head is completely between the needle guard wings. (See Figure G)

Figure G

- When the plunger is pushed as far as it will go, keep pressure on the plunger head. Take the needle out of the skin and then let go of the skin.
- Slowly take your thumb off the plunger head. This will let the empty syringe move up until the entire needle is covered by the needle guard. (See Figure H)

Figure H

- When the needle is pulled out of the skin, there may be a little bleeding at the injection site. This is normal. You can press a cotton ball or gauze pad to the injection site if needed. Do not rub the injection site. You may cover the injection site with a small adhesive bandage, if necessary.

If the dose is 90 mg, you will receive either one 90 mg prefilled syringe or two 45 mg prefilled syringes. If you receive two 45 mg prefilled syringes for a 90 mg dose, you will need to give a second injection right after the first. Repeat Steps 1 to 3 for the second injection using a new syringe. Choose a different site for the second injection.

Step 4: Disposing of the syringes.

- Put the syringe in a FDA-cleared sharps disposal container right away after use. Do not throw away (dispose of) syringes in your household trash.
- If you do not have a FDA-cleared sharps disposal container, you may use a household container that is:
  - made of heavy-duty plastic.
  - can be closed with a tight-fitting, puncture-resistant lid, without sharps being able to come out.
  - upright and stable during use,
  - leak-resistant,
  - and properly labeled to warn of hazardous waste inside the container.
- When your sharps disposal container is almost full, you will need to follow your community guidelines for the right way to dispose of your sharps disposal container. There may be local or state laws about how to throw away syringes and needles. For more information about safe sharps disposal, and for specific information about sharps disposal in the state that you live in, go to the FDA's website at: http://www.fda.gov/safesharpsdisposal.
- Do not dispose of your sharps disposal container in your household trash unless your community guidelines permit this. Do not recycle your sharps disposal container.
- If you have any questions, talk to your healthcare provider or pharmacist.

Manufactured by:
Accord BioPharma Inc. 8041 Arco Corporate Drive, Suite 200, Raleigh, North Carolina (NC), 27617 USA
US License No. 2105

This Instructions for Use has been approved by the U.S. Food and Drug Administration.

Revised: 11/2025

Marketed by:
GSMS, Inc.
Camarillo, CA 93012 USA

PACKAGE LABEL.PRINCIPAL DISPLAY PANEL

Carton Label

45 mg/0.5 mL

(NDC 51407-929-11)

Carton Label

90 mg/mL
(NDC 51407-930-11)

Carton Label

130 mg/26 mL (5 mg/mL)

(NDC 51407-931-11)